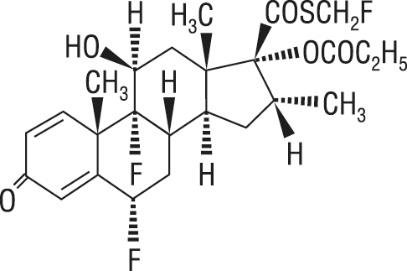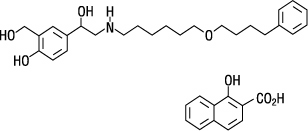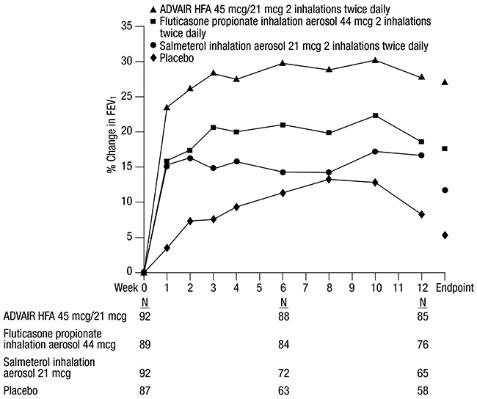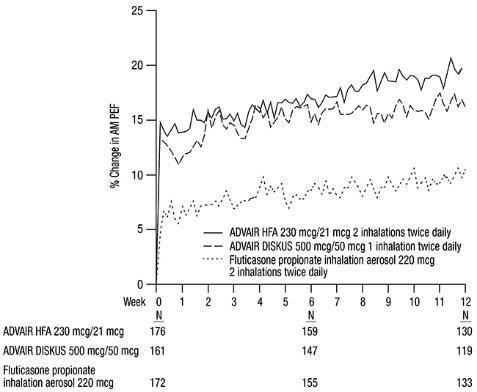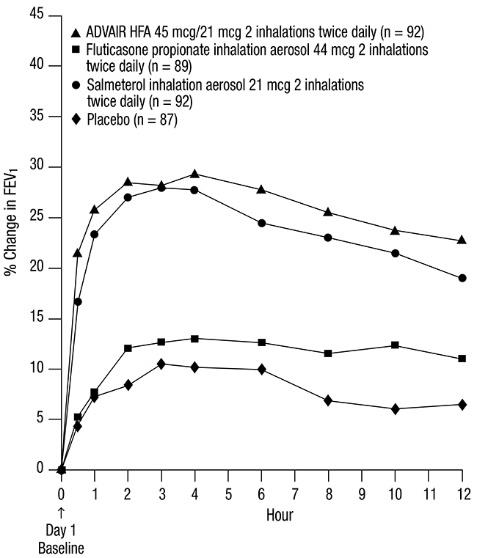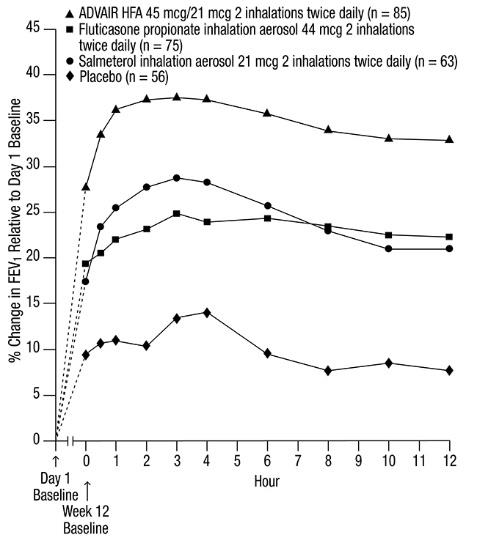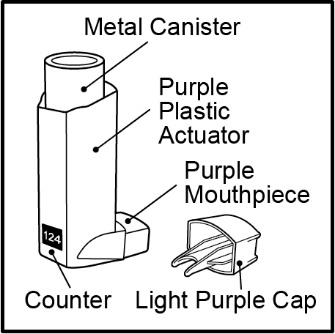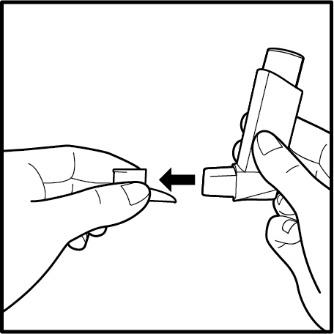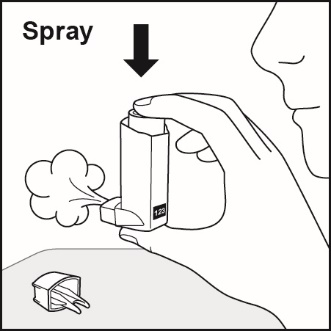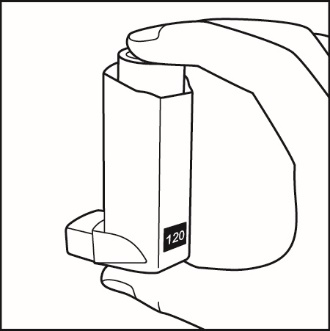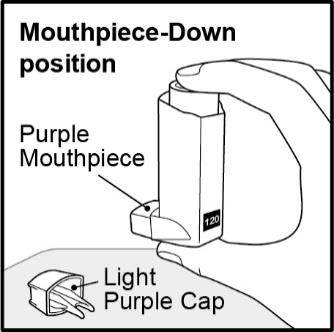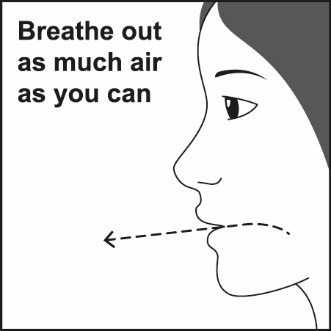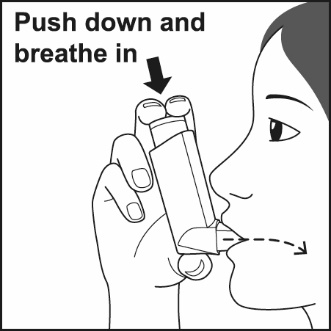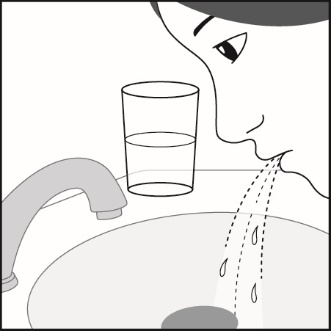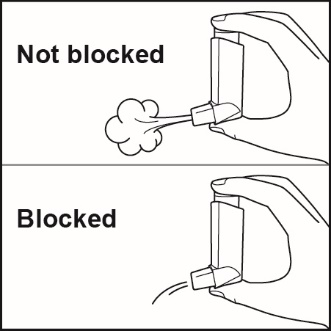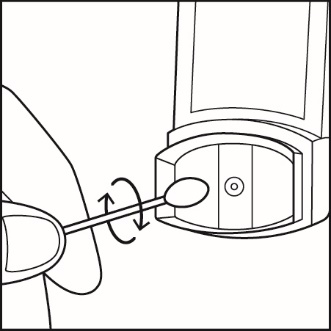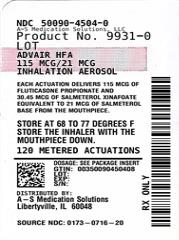 DRUG LABEL: ADVAIR HFA
NDC: 50090-4504 | Form: AEROSOL, METERED
Manufacturer: A-S Medication Solutions
Category: prescription | Type: HUMAN PRESCRIPTION DRUG LABEL
Date: 20250808

ACTIVE INGREDIENTS: FLUTICASONE PROPIONATE 115 ug/1 1; SALMETEROL XINAFOATE 21 ug/1 1
INACTIVE INGREDIENTS: NORFLURANE

HIGHLIGHTS OF PRESCRIBING INFORMATION

These highlights do not include all the information needed to use ADVAIR HFA safely and effectively. See full prescribing information for ADVAIR HFA.
ADVAIR HFA (fluticasone propionate and salmeterol inhalation aerosol), for oral inhalation use
Initial U.S. Approval: 2000

1 INDICATIONS AND USAGE

ADVAIR HFA is a combination of fluticasone propionate, an inhaled corticosteroid, and salmeterol, a long-acting beta2‑adrenergic agonist (LABA), indicated for treatment of asthma in adult and adolescent patients aged 12 years and older. (1)

Limitations of use: Not indicated for relief of acute bronchospasm. (1)

2 DOSAGE AND ADMINISTRATION

- For oral inhalation only. (2.1)
- Adult and adolescent patients aged 12 years and older: 2 inhalations of ADVAIR HFA 45 mcg/21 mcg, ADVAIR HFA 115 mcg/21 mcg, or ADVAIR HFA 230 mcg/21 mcg twice daily. (2.2)
- Starting dosage is based on asthma severity. (2.2)

3 DOSAGE FORMS AND STRENGTHS

Inhalation aerosol:

- 45 mcg fluticasone propionate/21 mcg salmeterol per actuation (3)
- 115 mcg fluticasone propionate/21 mcg salmeterol per actuation (3)
- 230 mcg fluticasone propionate/21 mcg salmeterol per actuation (3)

4 CONTRAINDICATIONS

- Primary treatment of status asthmaticus or acute episodes of asthma requiring intensive measures. (4)
- Hypersensitivity to any ingredient. (4)

5 WARNINGS AND PRECAUTIONS

- LABA monotherapy increases the risk of serious asthma-related events. (5.1)
- Do not initiate in acutely deteriorating asthma or to treat acute symptoms. (5.2)
- Do not use in combination with an additional medicine containing a LABA because of risk of overdose. (5.3)
- Candida albicans infection of the mouth and pharynx may occur. Monitor patients periodically. Advise the patient to rinse his/her mouth with water without swallowing after inhalation to help reduce the risk. (5.4)
- Increased risk of pneumonia in patients with COPD. Monitor patients for signs and symptoms of pneumonia. (5.5)
- Potential worsening of infections (e.g., existing tuberculosis; fungal, bacterial, viral, or parasitic infections; ocular herpes simplex). Use with caution in patients with these infections. More serious or even fatal course of chickenpox or measles can occur in susceptible patients. (5.6)
- Risk of impaired adrenal function when transferring from systemic corticosteroids. Taper patients slowly from systemic corticosteroids if transferring to ADVAIR HFA. (5.7)
- Hypercorticism and adrenal suppression may occur with very high dosages or at the regular dosage in susceptible individuals. If such changes occur, discontinue ADVAIR HFA slowly. (5.8)
- If paradoxical bronchospasm occurs, discontinue ADVAIR HFA and institute alternative therapy. (5.10)
- Use with caution in patients with cardiovascular or central nervous system disorders because of beta-adrenergic stimulation. (5.12)
- Assess for decrease in bone mineral density initially and periodically thereafter. (5.13)
- Monitor growth of pediatric patients. (5.14)
- Glaucoma and cataracts may occur with long-term use of inhaled corticosteroids. Consider referral to an ophthalmologist in patients who develop ocular symptoms or use ADVAIR HFA long term. (5.15)
- Be alert to eosinophilic conditions, hypokalemia, and hyperglycemia. (5.16, 5.18)
- Use with caution in patients with convulsive disorders, thyrotoxicosis, diabetes mellitus, and ketoacidosis. (5.17)

6 ADVERSE REACTIONS

Most common adverse reactions (incidence ≥3%) include: upper respiratory tract infection or inflammation, throat irritation, dysphonia, headache, dizziness, nausea and vomiting. (6.1)

To report SUSPECTED ADVERSE REACTIONS, contact GlaxoSmithKline at 1-888-825-5249 or FDA at 1-800-FDA-1088 or www.fda.gov/medwatch.

7 DRUG INTERACTIONS

- Strong cytochrome P450 3A4 inhibitors (e.g., ritonavir, ketoconazole): Use not recommended. May increase risk of systemic corticosteroid and cardiovascular effects. (7.1)
- Monoamine oxidase inhibitors and tricyclic antidepressants: Use with extreme caution. May potentiate effect of salmeterol on vascular system. (7.2)
- Beta-blockers: Use with caution. May block bronchodilatory effects of beta-agonists and produce severe bronchospasm. (7.3)
- Diuretics: Use with caution. Electrocardiographic changes and/or hypokalemia associated with non–potassium-sparing diuretics may worsen with concomitant beta-agonists. (7.4)

8 USE IN SPECIFIC POPULATIONS

Hepatic impairment: Monitor patients for signs of increased drug exposure. (8.6)

FULL PRESCRIBING INFORMATION

1 INDICATIONS AND USAGE

ADVAIR HFA is indicated for treatment of asthma in adult and adolescent patients aged 12 years and older. ADVAIR HFA should be used for patients not adequately controlled on a long-term asthma control medication such as an inhaled corticosteroid (ICS) or whose disease warrants initiation of treatment with both an ICS and long-acting beta2-adrenergic agonist (LABA).

Limitations of Use

ADVAIR HFA is not indicated for the relief of acute bronchospasm.

2 DOSAGE AND ADMINISTRATION

2.1 Administration Information

ADVAIR HFA should be administered by the orally inhaled route only. After inhalation, rinse mouth with water without swallowing to help reduce the risk of oropharyngeal candidiasis.

Priming

Prime ADVAIR HFA before using for the first time by releasing 4 sprays into the air away from the face, shaking well for 5 seconds before each spray. In cases where the inhaler has not been used for more than 4 weeks or when it has been dropped, prime the inhaler again by releasing 2 sprays into the air away from the face, shaking well for 5 seconds before each spray. Avoid spraying in eyes.

2.2 Recommended Dosage

Adult and adolescent patients aged 12 years and older: 2 oral inhalations twice daily, approximately 12 hours apart.

The maximum recommended dosage is 2 inhalations of ADVAIR HFA 230 mcg/21 mcg twice daily.

General Dosing Recommendation

When choosing the starting dosage strength of ADVAIR HFA, consider the patients’ disease severity, based on their previous asthma therapy, including the ICS dosage, as well as the patients’ current control of asthma symptoms and risk of future exacerbation.

If asthma symptoms arise in the period between doses, an inhaled, short-acting beta2-agonist should be used for immediate relief.

Improvement in asthma control following inhaled administration of ADVAIR HFA can occur within 30 minutes of beginning treatment, although maximum benefit may not be achieved for 1 week or longer after starting treatment. Individual patients will experience a variable time to onset and degree of symptom relief.

For patients who do not respond adequately to the starting dosage after 2 weeks of therapy, replacing the current strength of ADVAIR HFA with a higher strength may provide additional improvement in asthma control.

If a previously effective dosage regimen fails to provide adequate improvement in asthma control, the therapeutic regimen should be reevaluated and additional therapeutic options (e.g., replacing the current strength of ADVAIR HFA with a higher strength, adding additional ICS, initiating oral corticosteroids) should be considered.

More frequent administration or a greater number of inhalations (more than 2 inhalations twice daily) of the prescribed strength of ADVAIR HFA is not recommended as some patients are more likely to experience adverse effects with higher doses of salmeterol. Patients using ADVAIR HFA should not use additional LABA for any reason. [See Warnings and Precautions (5.3, 5.12).]

3 DOSAGE FORMS AND STRENGTHS

Inhalation aerosol: purple plastic inhaler with a light purple cap containing a pressurized metered-dose aerosol canister containing 60 or 120 metered inhalations and fitted with a counter.

- 45 mcg fluticasone propionate/21 mcg salmeterol from the mouthpiece per actuation
- 115 mcg fluticasone propionate/21 mcg salmeterol from the mouthpiece per actuation
- 230 mcg fluticasone propionate/21 mcg salmeterol from the mouthpiece per actuation

4 CONTRAINDICATIONS

ADVAIR HFA is contraindicated in the following conditions:

- Primary treatment of status asthmaticus or other acute episodes of asthma where intensive measures are required [see Warnings and Precautions (5.2)].
- Hypersensitivity to any of the ingredients [see Warnings and Precautions (5.11), Adverse Reactions (6.2), Description (11)].

5 WARNINGS AND PRECAUTIONS

5.1 Serious Asthma-Related Events – Hospitalizations, Intubations, Death

Use of LABA as monotherapy (without ICS) for asthma is associated with an increased risk of asthma-related death [see Salmeterol Multicenter Asthma Research Trial (SMART)]. Available data from controlled clinical trials also suggest that use of LABA as monotherapy increases the risk of asthma-related hospitalization in pediatric and adolescent patients. These findings are considered a class effect of LABA monotherapy. When LABA are used in fixed-dose combination with ICS, data from large clinical trials do not show a significant increase in the risk of serious asthma-related events (hospitalizations, intubations, death) compared with ICS alone (see Serious Asthma-Related Events with Inhaled Corticosteroid/Long-acting Beta2-adrenergic Agonists).

Serious Asthma-Related Events with Inhaled Corticosteroid/Long-acting Beta2-adrenergic Agonists

Four (4) large, 26-week, randomized, double-blind, active-controlled clinical safety trials were conducted to evaluate the risk of serious asthma-related events when LABA were used in fixed‑dose combination with ICS compared with ICS alone in subjects with asthma. Three (3) trials included adult and adolescent subjects aged 12 years and older: 1 trial compared fluticasone propionate/salmeterol inhalation powder with fluticasone propionate inhalation powder, 1 trial compared mometasone furoate/formoterol with mometasone furoate, and 1 trial compared budesonide/formoterol with budesonide. The fourth trial included pediatric subjects aged 4 to 11 years and compared fluticasone propionate/salmeterol inhalation powder with fluticasone propionate inhalation powder. The primary safety endpoint for all 4 trials was serious asthma-related events (hospitalizations, intubations, death). A blinded adjudication committee determined whether events were asthma related.

The 3 adult and adolescent trials were designed to rule out a risk margin of 2.0, and the pediatric trial was designed to rule out a risk margin of 2.7. Each individual trial met its pre-specified objective and demonstrated non-inferiority of ICS/LABA to ICS alone. A meta-analysis of the 3 adult and adolescent trials did not show a significant increase in risk of a serious asthma-related event with ICS/LABA fixed-dose combination compared with ICS alone (Table 1). These trials were not designed to rule out all risk for serious asthma-related events with ICS/LABA compared with ICS.

Table 1. Meta-analysis of Serious Asthma-Related Events in Subjects with Asthma Aged 12 Years and Older
 | ICS/LABA; (n = 17,537)a | ICS; (n = 17,552)a | ICS/LABA vs. ICS; Hazard Ratio; (95% CI)b
Serious asthma-related eventc | 116 | 105 | 1.10 (0.85, 1.44)
Asthma-related death | 2 | 0
Asthma-related intubation (endotracheal) | 1 | 2
Asthma-related hospitalization (≥24-hour stay) | 115 | 105
ICS = Inhaled Corticosteroid; LABA = Long-acting Beta2-adrenergic Agonist.
a Randomized subjects who had taken at least 1 dose of study drug. Planned treatment used for analysis.
b Estimated using a Cox proportional hazards model for time to first event with baseline hazards stratified by each of the 3 trials.
c Number of subjects with event that occurred within 6 months after the first use of study drug or 7 days after the last date of study drug, whichever date was later. Subjects can have one or more events, but only the first event was counted for analysis. A single, blinded, independent adjudication committee determined whether events were asthma related.

The pediatric safety trial included 6,208 pediatric subjects aged 4 to 11 years who received ICS/LABA (fluticasone propionate/salmeterol inhalation powder) or ICS (fluticasone propionate inhalation powder). In this trial, 27/3,107 (0.9%) subjects randomized to ICS/LABA and 21/3,101 (0.7%) subjects randomized to ICS experienced a serious asthma-related event. There were no asthma-related deaths or intubations. ICS/LABA did not show a significantly increased risk of a serious asthma-related event compared with ICS based on the pre-specified risk margin (2.7), with an estimated hazard ratio of time to first event of 1.29 (95% CI: 0.73, 2.27).

Salmeterol Multicenter Asthma Research Trial (SMART)

A 28-week, placebo-controlled, U.S. trial that compared the safety of salmeterol with placebo, each added to usual asthma therapy, showed an increase in asthma-related deaths in subjects receiving salmeterol (13/13,176 in subjects treated with salmeterol versus 3/13,179 in subjects treated with placebo; relative risk: 4.37 [95% CI: 1.25, 15.34]). Use of background ICS was not required in SMART. The increased risk of asthma‑related death is considered a class effect of LABA monotherapy.

5.2 Deterioration of Disease and Acute Episodes

ADVAIR HFA should not be initiated in patients during rapidly deteriorating or potentially life-threatening episodes of asthma. ADVAIR HFA has not been studied in subjects with acutely deteriorating asthma. The initiation of ADVAIR HFA in this setting is not appropriate.

Serious acute respiratory events, including fatalities, have been reported when salmeterol, a component of ADVAIR HFA, has been initiated in patients with significantly worsening or acutely deteriorating asthma. In most cases, these have occurred in patients with severe asthma (e.g., patients with a history of corticosteroid dependence, low pulmonary function, intubation, mechanical ventilation, frequent hospitalizations, previous life-threatening acute asthma exacerbations) and in some patients with acutely deteriorating asthma (e.g., patients with significantly increasing symptoms; increasing need for inhaled, short-acting beta2-agonists; decreasing response to usual medications; increasing need for systemic corticosteroids; recent emergency room visits; deteriorating lung function). However, these events have occurred in a few patients with less severe asthma as well. It was not possible from these reports to determine whether salmeterol contributed to these events.

Increasing use of inhaled, short-acting beta2-agonists is a marker of deteriorating asthma. In this situation, the patient requires immediate reevaluation with reassessment of the treatment regimen, giving special consideration to the possible need for replacing the current strength of ADVAIR HFA with a higher strength, adding additional ICS, or initiating systemic corticosteroids. Patients should not use more than 2 inhalations twice daily of ADVAIR HFA.

ADVAIR HFA should not be used for the relief of acute symptoms, i.e., as rescue therapy for the treatment of acute episodes of bronchospasm. ADVAIR HFA has not been studied in the relief of acute symptoms and extra doses should not be used for that purpose. Acute symptoms should be treated with an inhaled, short-acting beta2-agonist.

When beginning treatment with ADVAIR HFA, patients who have been taking oral or inhaled, short-acting beta2-agonists on a regular basis (e.g., 4 times a day) should be instructed to discontinue the regular use of these drugs.

5.3 Avoid Excessive Use of ADVAIR HFA and Avoid Use with Other Long-acting Beta2-agonists

ADVAIR HFA should not be used more often than recommended, at higher doses than recommended, or in conjunction with other medicines containing LABA, as an overdose may result. Clinically significant cardiovascular effects and fatalities have been reported in association with excessive use of inhaled sympathomimetic drugs. Patients using ADVAIR HFA should not use another medicine containing a LABA (e.g., salmeterol, formoterol fumarate, arformoterol tartrate, indacaterol) for any reason.

5.4 Oropharyngeal Candidiasis

In clinical trials, the development of localized infections of the mouth and pharynx with Candida albicans has occurred in subjects treated with ADVAIR HFA. When such an infection develops, it should be treated with appropriate local or systemic (i.e., oral) antifungal therapy while treatment with ADVAIR HFA continues, but at times therapy with ADVAIR HFA may need to be interrupted. Advise the patient to rinse his/her mouth with water without swallowing following inhalation to help reduce the risk of oropharyngeal candidiasis.

5.5 Pneumonia

Lower respiratory tract infections, including pneumonia, have been reported in patients with chronic obstructive pulmonary disease (COPD) following the inhaled administration of corticosteroids, including fluticasone propionate and ADVAIR DISKUS. In 2 replicate 1-year trials in 1,579 subjects with COPD, there was a higher incidence of pneumonia reported in subjects receiving ADVAIR DISKUS 250 mcg/50 mcg (7%) than in those receiving salmeterol 50 mcg (3%). The incidence of pneumonia in the subjects treated with ADVAIR DISKUS was higher in subjects older than 65 years (9%) compared with the incidence in subjects younger than 65 years (4%).

In a 3-year trial in 6,184 subjects with COPD, there was a higher incidence of pneumonia reported in subjects receiving ADVAIR DISKUS 500 mcg/50 mcg compared with placebo (16% with ADVAIR DISKUS 500 mcg/50 mcg, 14% with fluticasone propionate 500 mcg, 11% with salmeterol 50 mcg, and 9% with placebo). Similar to what was seen in the 1-year trials with ADVAIR DISKUS 250 mcg/50 mcg, the incidence of pneumonia was higher in subjects older than 65 years (18% with ADVAIR DISKUS 500 mcg/50 mcg versus 10% with placebo) compared with subjects younger than 65 years (14% with ADVAIR DISKUS 500 mcg/50 mcg versus 8% with placebo).

5.6 Immunosuppression and Risk of Infections

Persons who are using drugs that suppress the immune system are more susceptible to infections than healthy individuals. Chickenpox and measles, for example, can have a more serious or even fatal course in susceptible children or adults using corticosteroids. In such children or adults who have not had these diseases or been properly immunized, particular care should be taken to avoid exposure. How the dose, route, and duration of corticosteroid administration affect the risk of developing a disseminated infection is not known. The contribution of the underlying disease and/or prior corticosteroid treatment to the risk is also not known. If a patient is exposed to chickenpox, prophylaxis with varicella zoster immune globulin (VZIG) may be indicated. If a patient is exposed to measles, prophylaxis with pooled intramuscular immunoglobulin (IG) may be indicated. (See the respective package inserts for complete VZIG and IG prescribing information.) If chickenpox develops, treatment with antiviral agents may be considered.

ICS should be used with caution, if at all, in patients with active or quiescent tuberculosis infections of the respiratory tract; systemic fungal, bacterial, viral, or parasitic infections; or ocular herpes simplex.

5.7 Transferring Patients from Systemic Corticosteroid Therapy

HPA Suppression/Adrenal Insufficiency

Particular care is needed for patients who have been transferred from systemically active corticosteroids to ICS because deaths due to adrenal insufficiency have occurred in patients with asthma during and after transfer from systemic corticosteroids to less systemically available ICS. After withdrawal from systemic corticosteroids, a number of months are required for recovery of hypothalamic-pituitary-adrenal (HPA) function.

Patients who have been previously maintained on 20 mg or more of prednisone (or its equivalent) may be most susceptible, particularly when their systemic corticosteroids have been almost completely withdrawn. During this period of HPA suppression, patients may exhibit signs and symptoms of adrenal insufficiency when exposed to trauma, surgery, or infection (particularly gastroenteritis) or other conditions associated with severe electrolyte loss. Although ADVAIR HFA may control asthma symptoms during these episodes, in recommended doses it supplies less than normal physiological amounts of glucocorticoid systemically and does NOT provide the mineralocorticoid activity that is necessary for coping with these emergencies.

During periods of stress or a severe asthma attack, patients who have been withdrawn from systemic corticosteroids should be instructed to resume oral corticosteroids (in large doses) immediately and to contact their physicians for further instruction. These patients should also be instructed to carry a warning card indicating that they may need supplementary systemic corticosteroids during periods of stress or a severe asthma attack.

Patients requiring oral corticosteroids should be weaned slowly from systemic corticosteroid use after transferring to ADVAIR HFA. Prednisone reduction can be accomplished by reducing the daily prednisone dose by 2.5 mg on a weekly basis during therapy with ADVAIR HFA. Lung function (mean forced expiratory volume in 1 second [FEV1] or morning peak expiratory flow [AM PEF]), beta-agonist use, and asthma symptoms should be carefully monitored during withdrawal of oral corticosteroids. In addition, patients should be observed for signs and symptoms of adrenal insufficiency, such as fatigue, lassitude, weakness, nausea and vomiting, and hypotension.

Unmasking of Allergic Conditions Previously Suppressed by Systemic Corticosteroids

Transfer of patients from systemic corticosteroid therapy to ADVAIR HFA may unmask allergic conditions previously suppressed by the systemic corticosteroid therapy (e.g., rhinitis, conjunctivitis, eczema, arthritis, eosinophilic conditions).

Corticosteroid Withdrawal Symptoms

During withdrawal from oral corticosteroids, some patients may experience symptoms of systemically active corticosteroid withdrawal (e.g., joint and/or muscular pain, lassitude, depression) despite maintenance or even improvement of respiratory function.

5.8 Hypercorticism and Adrenal Suppression

Fluticasone propionate, a component of ADVAIR HFA, will often help control asthma symptoms with less suppression of HPA function than therapeutically equivalent oral doses of prednisone. Since fluticasone propionate is absorbed into the circulation and can be systemically active at higher doses, the beneficial effects of ADVAIR HFA in minimizing HPA dysfunction may be expected only when recommended dosages are not exceeded and individual patients are titrated to the lowest effective dose. A relationship between plasma levels of fluticasone propionate and inhibitory effects on stimulated cortisol production has been shown after 4 weeks of treatment with fluticasone propionate inhalation aerosol. Since individual sensitivity to effects on cortisol production exists, physicians should consider this information when prescribing ADVAIR HFA.

Because of the possibility of significant systemic absorption of ICS in sensitive patients, patients treated with ADVAIR HFA should be observed carefully for any evidence of systemic corticosteroid effects. Particular care should be taken in observing patients postoperatively or during periods of stress for evidence of inadequate adrenal response.

It is possible that systemic corticosteroid effects such as hypercorticism and adrenal suppression (including adrenal crisis) may appear in a small number of patients who are sensitive to these effects. If such effects occur, ADVAIR HFA should be reduced slowly, consistent with accepted procedures for reducing systemic corticosteroids, and other treatments for management of asthma symptoms should be considered.

5.9 Drug Interactions with Strong Cytochrome P450 3A4 Inhibitors

The use of strong cytochrome P450 3A4 (CYP3A4) inhibitors (e.g., ritonavir, atazanavir, clarithromycin, indinavir, itraconazole, nefazodone, nelfinavir, saquinavir, ketoconazole, telithromycin) with ADVAIR HFA is not recommended because increased systemic corticosteroid and increased cardiovascular adverse effects may occur [see Drug Interactions (7.1), Clinical Pharmacology (12.3)].

5.10 Paradoxical Bronchospasm and Upper Airway Symptoms

As with other inhaled medicines, ADVAIR HFA can produce paradoxical bronchospasm, which may be life threatening. If paradoxical bronchospasm occurs following dosing with ADVAIR HFA, it should be treated immediately with an inhaled, short-acting bronchodilator; ADVAIR HFA should be discontinued immediately; and alternative therapy should be instituted. Upper airway symptoms of laryngeal spasm, irritation, or swelling, such as stridor and choking, have been reported in patients receiving ADVAIR HFA.

5.11 Hypersensitivity Reactions, including Anaphylaxis

Immediate hypersensitivity reactions (e.g., urticaria, angioedema, rash, bronchospasm, hypotension), including anaphylaxis, may occur after administration of ADVAIR HFA [see Contraindications (4)].

5.12 Cardiovascular and Central Nervous System Effects

Excessive beta-adrenergic stimulation has been associated with seizures, angina, hypertension or hypotension, tachycardia with rates up to 200 beats/min, arrhythmias, nervousness, headache, tremor, palpitation, nausea, dizziness, fatigue, malaise, and insomnia [see Overdosage (10)]. Therefore, ADVAIR HFA, like all products containing sympathomimetic amines, should be used with caution in patients with cardiovascular disorders, especially coronary insufficiency, cardiac arrhythmias, and hypertension.

Salmeterol, a component of ADVAIR HFA, can produce a clinically significant cardiovascular effect in some patients as measured by pulse rate, blood pressure, and/or symptoms. Although such effects are uncommon after administration of salmeterol at recommended doses, if they occur, the drug may need to be discontinued. In addition, beta-agonists have been reported to produce electrocardiogram (ECG) changes, such as flattening of the T wave, prolongation of the QTc interval, and ST segment depression. The clinical significance of these findings is unknown. Large doses of inhaled or oral salmeterol (12 to 20 times the recommended dose) have been associated with clinically significant prolongation of the QTc interval, which has the potential for producing ventricular arrhythmias. Fatalities have been reported in association with excessive use of inhaled sympathomimetic drugs.

5.13 Reduction in Bone Mineral Density

Decreases in bone mineral density (BMD) have been observed with long-term administration of products containing ICS. The clinical significance of small changes in BMD with regard to long-term consequences such as fracture is unknown. Patients with major risk factors for decreased bone mineral content, such as prolonged immobilization, family history of osteoporosis, postmenopausal status, tobacco use, advanced age, poor nutrition, or chronic use of drugs that can reduce bone mass (e.g., anticonvulsants, oral corticosteroids), should be monitored and treated with established standards of care.

2-Year Fluticasone Propionate Trial

A 2-year trial in 160 subjects (females aged 18 to 40 years, males 18 to 50) with asthma receiving chlorofluorocarbon (CFC)-propelled fluticasone propionate inhalation aerosol 88 or 440 mcg twice daily demonstrated no statistically significant changes in BMD at any time point (24, 52, 76, and 104 weeks of double-blind treatment) as assessed by dual-energy x-ray absorptiometry at lumbar regions L1 through L4.

5.14 Effect on Growth

Orally inhaled corticosteroids may cause a reduction in growth velocity when administered to pediatric patients. Monitor the growth of pediatric patients receiving ADVAIR HFA routinely (e.g., via stadiometry). To minimize the systemic effects of orally inhaled corticosteroids, including ADVAIR HFA, titrate each patient’s dosage to the lowest dosage that effectively controls his/her symptoms [see Dosage and Administration (2), Use in Specific Populations (8.4)].

5.15 Glaucoma and Cataracts

Glaucoma, increased intraocular pressure, and cataracts have been reported in patients with asthma following the long-term administration of ICS, including fluticasone propionate, a component of ADVAIR HFA. Consider referral to an ophthalmologist in patients who develop ocular symptoms or use ADVAIR HFA long term [see Adverse Reactions (6)].

5.16 Eosinophilic Conditions and Churg-Strauss Syndrome

In rare cases, patients on inhaled fluticasone propionate, a component of ADVAIR HFA, may present with systemic eosinophilic conditions. Some of these patients have clinical features of vasculitis consistent with Churg-Strauss syndrome, a condition that is often treated with systemic corticosteroid therapy. These events usually, but not always, have been associated with the reduction and/or withdrawal of oral corticosteroid therapy following the introduction of fluticasone propionate. Cases of serious eosinophilic conditions have also been reported with other ICS in this clinical setting. Physicians should be alert to eosinophilia, vasculitic rash, worsening pulmonary symptoms, cardiac complications, and/or neuropathy presenting in their patients. A causal relationship between fluticasone propionate and these underlying conditions has not been established.

5.17 Coexisting Conditions

ADVAIR HFA, like all medicines containing sympathomimetic amines, should be used with caution in patients with convulsive disorders or thyrotoxicosis and in those who are unusually responsive to sympathomimetic amines. Large doses of the related beta2-adrenoceptor agonist albuterol, when administered intravenously, have been reported to aggravate preexisting diabetes mellitus and ketoacidosis.

5.18 Hypokalemia and Hyperglycemia

Beta-adrenergic agonist medicines may produce significant hypokalemia in some patients, possibly through intracellular shunting, which has the potential to produce adverse cardiovascular effects [see Clinical Pharmacology (12.2)]. The decrease in serum potassium is usually transient, not requiring supplementation. Clinically significant changes in blood glucose and/or serum potassium were seen infrequently during clinical trials with ADVAIR HFA at recommended doses.

6 ADVERSE REACTIONS

The following clinically significant adverse reactions are described elsewhere in the labeling:

- Serious asthma-related events – hospitalizations, intubations, death [see Warnings and Precautions (5.1)]
- Oropharyngeal candidiasis [see Warnings and Precautions (5.4)]
- Pneumonia in patients with COPD [see Warnings and Precautions (5.5)]
- Immunosuppression and risk of infections [see Warnings and Precautions (5.6)]
- Hypercorticism and adrenal suppression [see Warnings and Precautions (5.8)]
- Cardiovascular and central nervous system effects [see Warnings and Precautions (5.12)]
- Reduction in bone mineral density [see Warnings and Precautions (5.13)]
- Growth effects [see Warnings and Precautions (5.14)]
- Glaucoma and cataracts [see Warnings and Precautions (5.15)]

6.1 Clinical Trials Experience

Because clinical trials are conducted under widely varying conditions, adverse reaction rates observed in the clinical trials of a drug cannot be directly compared with rates in the clinical trials of another drug and may not reflect the rates observed in practice.

Adult and Adolescent Subjects Aged 12 Years and Older

The incidence of adverse reactions associated with ADVAIR HFA in Table 2 is based upon two 12-week, placebo-controlled, U.S. clinical trials (Trials 1 and 3) and 1 active-controlled 12-week U.S. clinical trial (Trial 2). A total of 1,008 adult and adolescent subjects with asthma (556 females and 452 males) previously treated with albuterol alone, salmeterol, or ICS were treated twice daily with 2 inhalations of ADVAIR HFA 45 mcg/21 mcg or ADVAIR HFA 115 mcg/21 mcg, fluticasone propionate CFC inhalation aerosol (44- or 110-mcg doses), salmeterol CFC inhalation aerosol 21 mcg, or placebo HFA inhalation aerosol. The average duration of exposure was 71 to 81 days in the active treatment groups compared with 51 days in the placebo group.

Table 2. Adverse Reactions with ADVAIR HFA with ≥3% Incidence in Adult and Adolescent Subjects with Asthma
Adverse Event | ADVAIR HFA |  | Fluticasone Propionate CFC Inhalation Aerosol |  | Salmeterol CFC Inhalation Aerosol | Placebo HFA Inhalation Aerosol
Adverse Event | 45 mcg/21 mcg (n = 187) % | 115 mcg/21 mcg (n = 94) % | 44 mcg (n = 186) % | 110 mcg (n = 91) % | 21 mcg (n = 274) % | (n = 176) %
Ear, nose, and throat
Upper respiratory tract infection | 16 | 24 | 13 | 15 | 17 | 13
Throat irritation | 9 | 7 | 12 | 13 | 9 | 7
Upper respiratory inflammation | 4 | 4 | 3 | 7 | 5 | 3
Hoarseness/dysphonia | 3 | 1 | 2 | 0 | 1 | 0
Lower respiratory
Viral respiratory infection | 3 | 5 | 4 | 5 | 3 | 4
Neurology
Headache | 21 | 15 | 24 | 16 | 20 | 11
Dizziness | 4 | 1 | 1 | 0 | <1 | 0
Gastrointestinal
Nausea and vomiting | 5 | 3 | 4 | 2 | 2 | 3
Viral gastrointestinal infection | 4 | 2 | 2 | 0 | 1 | 2
Gastrointestinal signs and symptoms | 3 | 2 | 2 | 1 | 1 | 1
Musculoskeletal
Musculoskeletal pain | 5 | 7 | 8 | 2 | 4 | 4
Muscle pain | 4 | 1 | 1 | 1 | 3 | <1

The incidence of common adverse reactions reported in Trial 4, a 12-week non-U.S. clinical trial in 509 subjects previously treated with ICS who were treated twice daily with 2 inhalations of ADVAIR HFA 230 mcg/21 mcg, fluticasone propionate CFC inhalation aerosol 220 mcg, or 1 inhalation of ADVAIR DISKUS 500 mcg/50 mcg was similar to the incidences reported in Table 2.

Additional Adverse Reactions

Other adverse reactions not previously listed, whether considered drug-related or not by the investigators, that occurred in the groups receiving ADVAIR HFA with an incidence of 1% to 3% and that occurred at a greater incidence than with placebo include the following: tachycardia, arrhythmias, myocardial infarction, postoperative complications, wounds and lacerations, soft tissue injuries, ear signs and symptoms, rhinorrhea/postnasal drip, epistaxis, nasal congestion/blockage, laryngitis, unspecified oropharyngeal plaques, dryness of nose, weight gain, allergic eye disorders, eye edema and swelling, gastrointestinal discomfort and pain, dental discomfort and pain, candidiasis mouth/throat, hyposalivation, gastrointestinal infections, disorders of hard tissue of teeth, abdominal discomfort and pain, oral abnormalities, arthralgia and articular rheumatism, muscle cramps and spasms, musculoskeletal inflammation, bone and skeletal pain, muscle injuries, sleep disorders, migraines, allergies and allergic reactions, viral infections, bacterial infections, candidiasis unspecified site, congestion, inflammation, bacterial reproductive infections, lower respiratory signs and symptoms, lower respiratory infections, lower respiratory hemorrhage, eczema, dermatitis and dermatosis, urinary infections.

Laboratory Test Abnormalities

In Trial 3, there were more reports of hyperglycemia among adults and adolescents receiving ADVAIR HFA, but this was not seen in Trials 1 and 2.

6.2 Postmarketing Experience

In addition to adverse reactions reported from clinical trials, the following adverse reactions have been identified during postapproval use of any formulation of ADVAIR, fluticasone propionate, and/or salmeterol regardless of indication. Because these reactions are reported voluntarily from a population of uncertain size, it is not always possible to reliably estimate their frequency or establish a causal relationship to drug exposure. These events have been chosen for inclusion due to either their seriousness, frequency of reporting, or causal connection to ADVAIR, fluticasone propionate, and/or salmeterol or a combination of these factors.

Cardiovascular

Arrhythmias (including atrial fibrillation, extrasystoles, supraventricular tachycardia), hypertension, ventricular tachycardia.

Ear, Nose, and Throat

Aphonia, earache, facial and oropharyngeal edema, paranasal sinus pain, rhinitis, throat soreness, tonsillitis.

Endocrine and Metabolic

Cushing’s syndrome, Cushingoid features, growth velocity reduction in children/adolescents, hypercorticism, osteoporosis.

Eye

Cataracts, glaucoma.

Gastrointestinal

Dyspepsia, xerostomia.

Hepatobiliary Tract and Pancreas

Abnormal liver function tests.

Immune System

Immediate and delayed hypersensitivity reactions, including rash and rare events of angioedema, bronchospasm, and anaphylaxis.

Infections and Infestations

Esophageal candidiasis.

Musculoskeletal

Back pain, myositis.

Neurology

Paresthesia, restlessness.

Non-Site Specific

Fever, pallor.

Psychiatry

Agitation, aggression, anxiety, depression. Behavioral changes, including hyperactivity and irritability, have been reported very rarely and primarily in children.

Respiratory

Asthma; asthma exacerbation; chest congestion; chest tightness; cough; dyspnea; immediate bronchospasm; influenza; paradoxical bronchospasm; tracheitis; wheezing; pneumonia; reports of upper respiratory symptoms of laryngeal spasm, irritation, or swelling such as stridor or choking.

Skin

Contact dermatitis, contusions, ecchymoses, photodermatitis, pruritus.

Urogenital

Dysmenorrhea, irregular menstrual cycle, pelvic inflammatory disease, vaginal candidiasis, vaginitis, vulvovaginitis.

7 DRUG INTERACTIONS

ADVAIR HFA has been used concomitantly with other drugs, including short-acting beta2-agonists, methylxanthines, and nasal corticosteroids, commonly used in patients with asthma without adverse drug reactions [see Clinical Pharmacology (12.2)]. No formal drug interaction trials have been performed with ADVAIR HFA.

7.1 Inhibitors of Cytochrome P450 3A4

Fluticasone propionate and salmeterol, the individual components of ADVAIR HFA, are substrates of CYP3A4. The use of strong CYP3A4 inhibitors (e.g., ritonavir, atazanavir, clarithromycin, indinavir, itraconazole, nefazodone, nelfinavir, saquinavir, ketoconazole, telithromycin) with ADVAIR HFA is not recommended because increased systemic corticosteroid and increased cardiovascular adverse effects may occur.

Ritonavir

Fluticasone Propionate: A drug interaction trial with fluticasone propionate aqueous nasal spray in healthy subjects has shown that ritonavir (a strong CYP3A4 inhibitor) can significantly increase plasma fluticasone propionate exposure, resulting in significantly reduced serum cortisol concentrations [see Clinical Pharmacology (12.3)]. During postmarketing use, there have been reports of clinically significant drug interactions in patients receiving fluticasone propionate and ritonavir, resulting in systemic corticosteroid effects including Cushing’s syndrome and adrenal suppression.

Ketoconazole

Fluticasone Propionate: Coadministration of orally inhaled fluticasone propionate (1,000 mcg) and ketoconazole (200 mg once daily) resulted in a 1.9-fold increase in plasma fluticasone propionate exposure and a 45% decrease in plasma cortisol area under the curve (AUC), but had no effect on urinary excretion of cortisol.

Salmeterol: In a drug interaction trial in 20 healthy subjects, coadministration of inhaled salmeterol (50 mcg twice daily) and oral ketoconazole (400 mg once daily) for 7 days resulted in greater systemic exposure to salmeterol (AUC increased 16-fold and Cmax increased 1.4-fold). Three (3) subjects were withdrawn due to beta2-agonist side effects (2 with prolonged QTc and 1 with palpitations and sinus tachycardia). Although there was no statistical effect on the mean QTc, coadministration of salmeterol and ketoconazole was associated with more frequent increases in QTc duration compared with salmeterol and placebo administration.

7.2 Monoamine Oxidase Inhibitors and Tricyclic Antidepressants

ADVAIR HFA should be administered with extreme caution to patients being treated with monoamine oxidase inhibitors or tricyclic antidepressants, or within 2 weeks of discontinuation of such agents, because the action of salmeterol, a component of ADVAIR HFA, on the vascular system may be potentiated by these agents.

7.3 Beta-adrenergic Receptor Blocking Agents

Beta-blockers not only block the pulmonary effect of beta-agonists, such as salmeterol, a component of ADVAIR HFA, but may also produce severe bronchospasm in patients with asthma. Therefore, patients with asthma should not normally be treated with beta-blockers. However, under certain circumstances, there may be no acceptable alternatives to the use of beta-adrenergic blocking agents for these patients; cardioselective beta-blockers could be considered, although they should be administered with caution.

7.4 Non–Potassium-Sparing Diuretics

The ECG changes and/or hypokalemia that may result from the administration of non–potassium-sparing diuretics (such as loop or thiazide diuretics) can be acutely worsened by beta-agonists, such as salmeterol, a component of ADVAIR HFA, especially when the recommended dose of the beta-agonist is exceeded. Although the clinical significance of these effects is not known, caution is advised in the coadministration of ADVAIR HFA with non–potassium-sparing diuretics.

8 USE IN SPECIFIC POPULATIONS

8.1 Pregnancy

Risk Summary

There are insufficient data on the use of ADVAIR HFA or individual monoproducts, fluticasone propionate and salmeterol xinafoate, in pregnant women. There are clinical considerations with the use of ADVAIR HFA in pregnant women. (See Clinical Considerations.) In animals, teratogenicity characteristic of corticosteroids, decreased fetal body weight and/or skeletal variations, in rats, mice, and rabbits, was observed with subcutaneously administered maternal toxic doses of fluticasone propionate less than the maximum recommended human daily inhaled dose (MRHDID) on a mcg/m^2 basis. (See Data.) However, fluticasone propionate administered via inhalation to rats decreased fetal body weight but did not induce teratogenicity at a maternal toxic dose less than the MRHDID on a mcg/m^2 basis. (See Data.) Experience with oral corticosteroids suggests that rodents are more prone to teratogenic effects from corticosteroids than humans. Oral administration of salmeterol to pregnant rabbits caused teratogenicity characteristic of beta-adrenoceptor stimulation at maternal doses approximately 25 times the MRHDID on an AUC basis. These adverse effects generally occurred at large multiples of the MRHDID when salmeterol was administered by the oral route to achieve high systemic exposures. No such effects occurred at an oral salmeterol dose approximately 10 times the MRHDID. (See Data.)

The estimated risk of major birth defects and miscarriage for the indicated population is unknown. In the U.S. general population, the estimated risk of major birth defects and miscarriage in clinically recognized pregnancies is 2% to 4% and 15% to 20%, respectively.

Clinical Considerations

Disease-Associated Maternal and/or Embryofetal Risk: In women with poorly or moderately controlled asthma, there is an increased risk of several perinatal outcomes such as pre-eclampsia in the mother and prematurity, low birth weight, and small for gestational age in the neonate. Pregnant women should be closely monitored and medication adjusted as necessary to maintain optimal control of asthma.

Labor and Delivery: There are no human studies evaluating the effects of ADVAIR HFA during labor and delivery. Because of the potential for beta-agonist interference with uterine contractility, use of ADVAIR HFA during labor should be restricted to those patients in whom the benefits clearly outweigh the risks.

Data

Human Data: Fluticasone Propionate: Following inhaled administration, fluticasone propionate was detected in the neonatal cord blood after delivery.

Animal Data: Fluticasone Propionate and Salmeterol: In an embryofetal development study with pregnant rats that received the combination of subcutaneous administration of fluticasone propionate and oral administration of salmeterol at doses of 0/1,000; 30/0; 10/100; 30/1,000; and 100/10,000 mcg/kg/day (as fluticasone propionate/salmeterol) during the period of organogenesis, findings were generally consistent with the individual monoproducts and there was no exacerbation of expected fetal effects. Omphalocele, increased embryofetal deaths, decreased body weight, and skeletal variations were observed in rat fetuses in the presence of maternal toxicity when combining fluticasone propionate at a dose approximately equivalent to the MRHDID (on a mcg/m^2 basis at a maternal subcutaneous dose of 100 mcg/kg/day) and salmeterol at a dose approximately 1,200 times the MRHDID (on a mcg/m^2 basis at a maternal oral dose of 10,000 mcg/kg/day). The rat no observed adverse effect level (NOAEL) was observed when combining fluticasone propionate at a dose less than the MRHDID (on a mcg/m^2 basis at a maternal subcutaneous dose of 30 mcg/kg/day) and salmeterol at a dose approximately 120 times the MRHDID (on a mcg/m^2 basis at a maternal oral dose of 1,000 mcg/kg/day).

In an embryofetal development study with pregnant mice that received the combination of subcutaneous administration of fluticasone propionate and oral administration of salmeterol at doses of 0/1,400; 40/0; 10/200; 40/1,400; or 150/10,000 mcg/kg/day (as fluticasone propionate/salmeterol) during the period of organogenesis, findings were generally consistent with the individual monoproducts and there was no exacerbation of expected fetal effects. Cleft palate, fetal death, increased implantation loss, and delayed ossification were observed in mouse fetuses when combining fluticasone propionate at a dose approximately equivalent to the MRHDID (on a mcg/m^2 basis at a maternal subcutaneous dose of 150 mcg/kg/day) and salmeterol at a dose approximately 580 times the MRHDID (on a mcg/m^2 basis at a maternal oral dose of 10,000 mcg/kg/day). No developmental toxicity was observed at combination doses of fluticasone propionate up to approximately 0.2 times the MRHDID (on a mcg/m^2 basis at a maternal subcutaneous dose of 40 mcg/kg) and doses of salmeterol up to approximately 80 times the MRHDID (on a mcg/m^2 basis at a maternal oral dose of 1,400 mcg/kg).

Fluticasone Propionate: In embryofetal development studies with pregnant rats and mice dosed by the subcutaneous route throughout the period of organogenesis, fluticasone propionate was teratogenic in both species. Omphalocele, decreased body weight, and skeletal variations were observed in rat fetuses, in the presence of maternal toxicity, at a dose approximately equivalent to the MRHDID (on a mcg/m^2 basis with a maternal subcutaneous dose of 100 mcg/kg/day). The rat NOAEL was observed at approximately 0.3 times the MRHDID (on a mcg/m^2 basis with a maternal subcutaneous dose of 30 mcg/kg/day). Cleft palate and fetal skeletal variations were observed in mouse fetuses at a dose approximately 0.2 times the MRHDID (on a mcg/m^2 basis with a maternal subcutaneous dose of 45 mcg/kg/day). The mouse NOAEL was observed with a dose approximately 0.08 times the MRHDID (on a mcg/m^2 basis with a maternal subcutaneous dose of 15 mcg/kg/day).

In an embryofetal development study with pregnant rats dosed by the inhalation route throughout the period of organogenesis, fluticasone propionate produced decreased fetal body weights and skeletal variations, in the presence of maternal toxicity, at a dose approximately 0.3 times the MRHDID (on a mcg/m^2 basis with a maternal inhalation dose of 25.7 mcg/kg/day); however, there was no evidence of teratogenicity. The NOAEL was observed with a dose approximately 0.05 times the MRHDID (on a mcg/m^2 basis with a maternal inhalation dose of 5.5 mcg/kg/day).

In an embryofetal development study in pregnant rabbits that were dosed by the subcutaneous route throughout organogenesis, fluticasone propionate produced reductions of fetal body weights, in the presence of maternal toxicity, at doses less than the MRHDID (on a mcg/m^2 basis with a maternal subcutaneous dose of 0.57 mcg/kg/day). Teratogenicity was evident based upon a finding of cleft palate for 1 fetus at a dose approximately 0.09 times the MRHDID (on a mcg/m^2 basis with a maternal subcutaneous dose of 4 mcg/kg/day). The NOAEL was observed in rabbit fetuses with a dose approximately 0.002 times the MRHDID (on a mcg/m^2 basis with a maternal subcutaneous dose of 0.08 mcg/kg/day).

Fluticasone propionate crossed the placenta following subcutaneous administration to mice and rats and oral administration to rabbits.

In a pre- and post-natal development study in pregnant rats dosed by the subcutaneous route from late gestation through delivery and lactation (Gestation Day 17 to Postpartum Day 22), fluticasone propionate was not associated with decreases in pup body weight and had no effects on developmental landmarks, learning, memory, reflexes, or fertility at doses up to 0.5 times the MRHDID (on a mcg/m^2 basis with maternal subcutaneous doses up to 50 mcg/kg/day).

Salmeterol: In 3 embryofetal development studies, pregnant rabbits received oral administration of salmeterol at doses ranging from 100 to 10,000 mcg/kg/day during the period of organogenesis. In pregnant Dutch rabbits administered salmeterol doses approximately 25 times the MRHDID (on an AUC basis at maternal oral doses of 1,000 mcg/kg/day and higher), fetal toxic effects were observed characteristically resulting from beta-adrenoceptor stimulation. These included precocious eyelid openings, cleft palate, sternebral fusion, limb and paw flexures, and delayed ossification of the frontal cranial bones. No such effects occurred at a salmeterol dose approximately 10 times the MRHDID (on an AUC basis at a maternal oral dose of 600 mcg/kg/day). New Zealand White rabbits were less sensitive since only delayed ossification of the frontal cranial bones was seen at a salmeterol dose approximately 2,300 times the MRHDID (on a mcg/m^2 basis at a maternal oral dose of 10,000 mcg/kg/day).

In 2 embryofetal development studies, pregnant rats received salmeterol by oral administration at doses ranging from 100 to 10,000 mcg/kg/day during the period of organogenesis. Salmeterol produced no maternal toxicity or embryofetal effects at doses up to approximately 1,200 times the MRHDID (on a mcg/m^2 basis at maternal oral doses up to 10,000 mcg/kg/day).

In a peri- and post-natal development study in pregnant rats dosed by the oral route from late gestation through delivery and lactation, salmeterol at a dose approximately 1,200 times the MRHDID (on a mcg/m^2 basis with a maternal oral dose of 10,000 mcg/kg/day) was fetotoxic and decreased the fertility of survivors.

Salmeterol xinafoate crossed the placenta following oral administration to mice and rats.

8.2 Lactation

Risk Summary

There are no available data on the presence of fluticasone propionate or salmeterol in human milk, the effects on the breastfed child, or the effects on milk production. Other corticosteroids have been detected in human milk. However, fluticasone propionate and salmeterol concentrations in plasma after inhaled therapeutic doses are low and therefore concentrations in human breast milk are likely to be correspondingly low [see Clinical Pharmacology (12.3)]. The developmental and health benefits of breastfeeding should be considered along with the mother’s clinical need for ADVAIR HFA and any potential adverse effects on the breastfed child from ADVAIR HFA or from the underlying maternal condition.

Data

Animal Data: Subcutaneous administration of tritiated fluticasone propionate at a dose of 10 mcg/kg/day to lactating rats resulted in measurable levels in milk. Oral administration of salmeterol at a dose of 10,000 mcg/kg/day to lactating rats resulted in measurable levels in milk.

8.4 Pediatric Use

The safety and effectiveness of ADVAIR HFA have been established in pediatric patients aged 12 years and older. Use of ADVAIR HFA in this age group is supported by evidence from adequate and well-controlled studies in adults with additional data from thirty-eight (38) subjects aged 12 to 17 years were treated with ADVAIR HFA in U.S. pivotal clinical trials. Subjects in this age group demonstrated efficacy results similar to those observed in subjects aged 18 years and older. There were no obvious differences in the type or frequency of adverse events reported in this age group compared with subjects aged 18 years and older.

In a 12-week trial, the safety of ADVAIR HFA 45 mcg/21 mcg given as 2 inhalations twice daily was compared with that of fluticasone propionate 44 mcg HFA (FLOVENT HFA) 2 inhalations twice daily in 350 subjects aged 4 to 11 years with persistent asthma currently being treated with ICS. No new safety concerns were observed in children aged 4 to 11 years treated for 12 weeks with ADVAIR HFA 45 mcg/21 mcg compared with adults and adolescents aged 12 years and older. Common adverse reactions (≥3%) seen in children aged 4 to 11 years treated with ADVAIR HFA 45 mcg/21 mcg but not reported in the adult and adolescent clinical trials of ADVAIR HFA include: pyrexia, cough, pharyngolaryngeal pain, rhinitis, and sinusitis [see Adverse Reactions (6.1)]. This trial was not designed to assess the effect of salmeterol, a component of ADVAIR HFA, on asthma hospitalizations and death in subjects aged 4 to 11 years.

The pharmacokinetics and pharmacodynamic effect on serum cortisol of 21 days of treatment with ADVAIR HFA 45 mcg/21 mcg (2 inhalations twice daily with or without a spacer) or ADVAIR DISKUS 100 mcg/50 mcg (1 inhalation twice daily) was evaluated in a trial of 31 children aged 4 to 11 years with mild asthma. Systemic exposure to salmeterol xinafoate was similar for ADVAIR HFA, ADVAIR HFA delivered with a spacer, and ADVAIR DISKUS while the systemic exposure to fluticasone propionate was lower with ADVAIR HFA compared with that of ADVAIR HFA delivered with a spacer or ADVAIR DISKUS. There were reductions in serum cortisol from baseline in all treatment groups (14%, 22%, and 13% for ADVAIR HFA, ADVAIR HFA delivered with a spacer, and ADVAIR DISKUS, respectively) [see Clinical Pharmacology (12.2, 12.3)].

The safety and effectiveness of ADVAIR HFA in pediatric patients younger than 12 years have not been established.

Effects on Growth

ICS, including fluticasone propionate, a component of ADVAIR HFA, may cause a reduction in growth velocity in children and adolescents [see Warnings and Precautions (5.14)]. The growth of pediatric patients receiving orally inhaled corticosteroids, including ADVAIR HFA, should be monitored.

A 52-week placebo-controlled trial to assess the potential growth effects of fluticasone propionate inhalation powder (FLOVENT ROTADISK) at 50 and 100 mcg twice daily was conducted in the U.S. in 325 prepubescent children (244 males and 81 females) aged 4 to 11 years. The mean growth velocities at 52 weeks observed in the intent-to-treat population were 6.32 cm/year in the placebo group (n = 76), 6.07 cm/year in the 50-mcg group (n = 98), and 5.66 cm/year in the 100-mcg group (n = 89). An imbalance in the proportion of children entering puberty between groups and a higher dropout rate in the placebo group due to poorly controlled asthma may be confounding factors in interpreting these data. A separate subset analysis of children who remained prepubertal during the trial revealed growth rates at 52 weeks of 6.10 cm/year in the placebo group (n = 57), 5.91 cm/year in the 50-mcg group (n = 74), and 5.67 cm/year in the 100-mcg group (n = 79). In children aged 8.5 years, the mean age of children in this trial, the range for expected growth velocity is: boys – 3rd percentile = 3.8 cm/year, 50th percentile = 5.4 cm/year, and 97th percentile = 7.0 cm/year; girls – 3rd percentile = 4.2 cm/year, 50th percentile = 5.7 cm/year, and 97th percentile = 7.3 cm/year. The clinical relevance of these growth data is not certain.

If a child or adolescent on any corticosteroid appears to have growth suppression, the possibility that he/she is particularly sensitive to this effect of corticosteroids should be considered. The potential growth effects of prolonged treatment should be weighed against the clinical benefits obtained. To minimize the systemic effects of orally inhaled corticosteroids, including ADVAIR HFA, each patient should be titrated to the lowest strength that effectively controls his/her asthma [see Dosage and Administration (2)].

8.5 Geriatric Use

Clinical trials of ADVAIR HFA did not include sufficient numbers of subjects aged 65 years and older to determine whether older subjects respond differently than younger subjects. In general, dose selection for an elderly patient should be cautious, usually starting at the low end of the dosing range, reflecting the greater frequency of decreased hepatic, renal, or cardiac function, and of concomitant disease or other drug therapy. In addition, as with other products containing beta2-agonists, special caution should be observed when using ADVAIR HFA in geriatric patients who have concomitant cardiovascular disease that could be adversely affected by beta2-agonists.

8.6 Hepatic Impairment

Formal pharmacokinetic studies using ADVAIR HFA have not been conducted in patients with hepatic impairment. However, since both fluticasone propionate and salmeterol are predominantly cleared by hepatic metabolism, impairment of liver function may lead to accumulation of fluticasone propionate and salmeterol in plasma. Therefore, patients with hepatic disease should be closely monitored.

8.7 Renal Impairment

Formal pharmacokinetic studies using ADVAIR HFA have not been conducted in patients with renal impairment.

10 OVERDOSAGE

No human overdosage data has been reported for ADVAIR HFA.

ADVAIR HFA contains both fluticasone propionate and salmeterol; therefore, the risks associated with overdosage for the individual components described below apply to ADVAIR HFA. Treatment of overdosage consists of discontinuation of ADVAIR HFA together with institution of appropriate symptomatic and/or supportive therapy. The judicious use of a cardioselective beta-receptor blocker may be considered, bearing in mind that such medication can produce bronchospasm. Cardiac monitoring is recommended in cases of overdosage.

Fluticasone Propionate

Chronic overdosage of fluticasone propionate may result in signs/symptoms of hypercorticism [see Warnings and Precautions (5.8)].

Salmeterol

The expected signs and symptoms with overdosage of salmeterol are those of excessive beta‑adrenergic stimulation and/or occurrence or exaggeration of any of the signs and symptoms of beta-adrenergic stimulation (e.g., seizures, angina, hypertension or hypotension, tachycardia with rates up to 200 beats/min, arrhythmias, nervousness, headache, tremor, muscle cramps, dry mouth, palpitation, nausea, dizziness, fatigue, malaise, insomnia, hyperglycemia, hypokalemia, metabolic acidosis). Overdosage with salmeterol can lead to clinically significant prolongation of the QTc interval, which can produce ventricular arrhythmias.

As with all inhaled sympathomimetic medicines, cardiac arrest and even death may be associated with an overdose of salmeterol.

11 DESCRIPTION

ADVAIR HFA 45 mcg/21 mcg, ADVAIR HFA 115 mcg/21 mcg, and ADVAIR HFA 230 mcg/21 mcg are combinations of fluticasone propionate and salmeterol xinafoate.

One active component of ADVAIR HFA is fluticasone propionate, a corticosteroid having the chemical name S-(fluoromethyl) 6α,9-difluoro-11β,17-dihydroxy-16α-methyl-3-oxoandrosta-1,4-diene-17β-carbothioate, 17-propionate and the following chemical structure:

Fluticasone propionate is a white powder with a molecular weight of 500.6, and the empirical formula is C25H31F3O5S. It is practically insoluble in water, freely soluble in dimethyl sulfoxide and dimethylformamide, and slightly soluble in methanol and 95% ethanol.

The other active component of ADVAIR HFA is salmeterol xinafoate, a beta2-adrenergic bronchodilator. Salmeterol xinafoate is the racemic form of the 1-hydroxy-2-naphthoic acid salt of salmeterol. It has the chemical name 4-hydroxy-α^1-[[[6-(4-phenylbutoxy)hexyl]amino]methyl]-1,3-benzenedimethanol, 1-hydroxy-2-naphthalenecarboxylate and the following chemical structure:

Salmeterol xinafoate is a white powder with a molecular weight of 603.8, and the empirical formula is C25H37NO4•C11H8O3. It is freely soluble in methanol; slightly soluble in ethanol, chloroform, and isopropanol; and sparingly soluble in water.

ADVAIR HFA is a purple plastic inhaler with a light purple cap containing a pressurized metered-dose aerosol canister fitted with a counter. Each canister contains a microcrystalline suspension of micronized fluticasone propionate and micronized salmeterol xinafoate in propellant HFA-134a (1,1,1,2-tetrafluoroethane). It contains no other excipients.

After priming, each actuation of the inhaler delivers 50, 125, or 250 mcg of fluticasone propionate and 25 mcg of salmeterol in 75 mg of suspension from the valve. Each actuation delivers 45, 115, or 230 mcg of fluticasone propionate and 21 mcg of salmeterol from the actuator. Twenty-one micrograms (21 mcg) of salmeterol base is equivalent to 30.45 mcg of salmeterol xinafoate. The actual amount of drug delivered to the lung will depend on patient factors, such as the coordination between the actuation of the inhaler and inspiration through the delivery system.

Prime ADVAIR HFA before using for the first time by releasing 4 sprays into the air away from the face, shaking well for 5 seconds before each spray. In cases where the inhaler has not been used for more than 4 weeks or when it has been dropped, prime the inhaler again by releasing 2 sprays into the air away from the face, shaking well for 5 seconds before each spray. Avoid spraying in eyes.

12 CLINICAL PHARMACOLOGY

12.1 Mechanism of Action

ADVAIR HFA

ADVAIR HFA contains both fluticasone propionate and salmeterol. The mechanisms of action described below for the individual components apply to ADVAIR HFA. These drugs represent 2 different classes of medications (a synthetic corticosteroid and a LABA) that have different effects on clinical, physiologic, and inflammatory indices of asthma.

Fluticasone Propionate

Fluticasone propionate is a synthetic trifluorinated corticosteroid with anti-inflammatory activity. Fluticasone propionate has been shown in vitro to exhibit a binding affinity for the human glucocorticoid receptor that is 18 times that of dexamethasone, almost twice that of beclomethasone-17-monopropionate (BMP), the active metabolite of beclomethasone dipropionate, and over 3 times that of budesonide. Data from the McKenzie vasoconstrictor assay in man are consistent with these results. The clinical significance of these findings is unknown.

Inflammation is an important component in the pathogenesis of asthma. Corticosteroids have been shown to have a wide range of actions on multiple cell types (e.g., mast cells, eosinophils, neutrophils, macrophages, lymphocytes) and mediators (e.g., histamine, eicosanoids, leukotrienes, cytokines) involved in inflammation. These anti-inflammatory actions of corticosteroids contribute to their efficacy in asthma.

Salmeterol Xinafoate

Salmeterol is a selective LABA. In vitro studies show salmeterol to be at least 50 times more selective for beta2‑adrenoceptors than albuterol. Although beta2-adrenoceptors are the predominant adrenergic receptors in bronchial smooth muscle and beta1-adrenoceptors are the predominant receptors in the heart, there are also beta2-adrenoceptors in the human heart comprising 10% to 50% of the total beta-adrenoceptors. The precise function of these receptors has not been established, but their presence raises the possibility that even selective beta2-agonists may have cardiac effects.

The pharmacologic effects of beta2-adrenoceptor agonist drugs, including salmeterol, are at least in part attributable to stimulation of intracellular adenyl cyclase, the enzyme that catalyzes the conversion of adenosine triphosphate (ATP) to cyclic-3′,5′-adenosine monophosphate (cyclic AMP). Increased cyclic AMP levels cause relaxation of bronchial smooth muscle and inhibition of release of mediators of immediate hypersensitivity from cells, especially from mast cells.

In vitro tests show that salmeterol is a potent and long-lasting inhibitor of the release of mast cell mediators, such as histamine, leukotrienes, and prostaglandin D2, from human lung. Salmeterol inhibits histamine-induced plasma protein extravasation and inhibits platelet-activating factor–induced eosinophil accumulation in the lungs of guinea pigs when administered by the inhaled route. In humans, single doses of salmeterol administered via inhalation aerosol attenuate allergen-induced bronchial hyper-responsiveness.

12.2 Pharmacodynamics

ADVAIR HFA

Healthy Subjects: Cardiovascular Effects: Since systemic pharmacodynamic effects of salmeterol are not normally seen at the therapeutic dose, higher doses were used to produce measurable effects. Four (4) placebo-controlled crossover trials were conducted with healthy subjects: (1) a cumulative-dose trial using 42 to 336 mcg of salmeterol CFC inhalation aerosol given alone or as ADVAIR HFA 115 mcg/21 mcg, (2) a single-dose trial using 4 inhalations of ADVAIR HFA 230 mcg/21 mcg, salmeterol CFC inhalation aerosol 21 mcg, or fluticasone propionate CFC inhalation aerosol 220 mcg, (3) a single-dose trial using 8 inhalations of ADVAIR HFA 45 mcg/21 mcg, ADVAIR HFA 115 mcg/21 mcg, or ADVAIR HFA 230 mcg/21 mcg, and (4) a single-dose trial using 4 inhalations of ADVAIR HFA 230 mcg/21 mcg; 2 inhalations of ADVAIR DISKUS 500 mcg/50 mcg; 4 inhalations of fluticasone propionate CFC inhalation aerosol 220 mcg; or 1,010 mcg of fluticasone propionate given intravenously. In these trials pulse rate, blood pressure, QTc interval, glucose, and/or potassium were measured. Comparable or lower effects were observed for ADVAIR HFA compared with ADVAIR DISKUS or salmeterol alone. The effect of salmeterol on pulse rate and potassium was not altered by the presence of different amounts of fluticasone propionate in ADVAIR HFA.

Hypothalamic-Pituitary-Adrenal Axis Effects: The potential effect of salmeterol on the effects of fluticasone propionate on the HPA axis was also evaluated in 3 of these trials. Compared with fluticasone propionate CFC inhalation aerosol, ADVAIR HFA had less effect on 24-hour urinary cortisol excretion and less or comparable effect on 24-hour serum cortisol. In these crossover trials in healthy subjects, ADVAIR HFA and ADVAIR DISKUS had similar effects on urinary and serum cortisol.

Subjects with Asthma: Cardiovascular Effects: In clinical trials with ADVAIR HFA in adult and adolescent subjects aged 12 years and older with asthma, systemic pharmacodynamic effects of salmeterol (pulse rate, blood pressure, QTc interval, potassium, and glucose) were similar to or slightly lower in patients treated with ADVAIR HFA compared with patients treated with salmeterol CFC inhalation aerosol 21 mcg. In 61 adult and adolescent subjects with asthma given ADVAIR HFA (45 mcg/21 mcg or 115 mcg/21 mcg), continuous 24-hour electrocardiographic monitoring was performed after the first dose and after 12 weeks of twice-daily therapy, and no clinically significant dysrhythmias were noted.

The effect of 21 days of treatment with ADVAIR HFA 45 mcg/21 mcg (2 inhalations twice daily with or without a spacer) or ADVAIR DISKUS 100 mcg/50 mcg (1 inhalation twice daily) was evaluated in 31 children aged 4 to 11 years with mild asthma. There were no notable changes from baseline for QTc, heart rate, or systolic and diastolic blood pressure.

Hypothalamic-Pituitary-Adrenal Axis Effects: A 4-way crossover trial in 13 subjects with asthma compared pharmacodynamics at steady state following 4 weeks of twice-daily treatment with 2 inhalations of ADVAIR HFA 115 mcg/21 mcg, 1 inhalation of ADVAIR DISKUS 250 mcg/50 mcg, 2 inhalations of fluticasone propionate HFA inhalation aerosol 110 mcg, and placebo. No significant differences in serum cortisol AUC were observed between active treatments and placebo. Mean 12-hour serum cortisol AUC ratios comparing active treatment with placebo ranged from 0.9 to 1.2. No statistically or clinically significant increases in heart rate or QTc interval were observed for any active treatment compared with placebo.

In a 12-week trial in adult and adolescent subjects with asthma, ADVAIR HFA 115 mcg/21 mcg was compared with the individual components, fluticasone propionate CFC inhalation aerosol 110 mcg and salmeterol CFC inhalation aerosol 21 mcg, and placebo [see Clinical Studies (14.1)]. All treatments were administered as 2 inhalations twice daily. After 12 weeks of treatment with these therapeutic doses, the geometric mean ratio of urinary cortisol excretion compared with baseline was 0.9 for ADVAIR HFA and fluticasone propionate and 1.0 for placebo and salmeterol. In addition, the ability to increase cortisol production in response to stress, as assessed by 30-minute cosyntropin stimulation in 23 to 32 subjects per treatment group, remained intact for the majority of subjects and was similar across treatments. Three (3) subjects who received ADVAIR HFA 115 mcg/21 mcg had an abnormal response (peak serum cortisol <18 mcg/dL) after dosing, compared with 1 subject who received placebo, 2 subjects who received fluticasone propionate 110 mcg, and 1 subject who received salmeterol.

In another 12-week trial in adult and adolescent subjects with asthma, ADVAIR HFA 230 mcg/21 mcg (2 inhalations twice daily) was compared with ADVAIR DISKUS 500 mcg/50 mcg (1 inhalation twice daily) and fluticasone propionate CFC inhalation aerosol 220 mcg (2 inhalations twice daily) [see Clinical Studies (14.1)]. The geometric mean ratio of 24‑hour urinary cortisol excretion at week 12 compared with baseline was 0.9 for all 3 treatment groups.

The effect of 21 days of treatment with ADVAIR HFA 45 mcg/21 mcg (2 inhalations twice daily with or without a spacer) or ADVAIR DISKUS 100 mcg/50 mcg (1 inhalation twice daily) on serum cortisol was evaluated in 31 children aged 4 to 11 years with mild asthma. There were reductions in serum cortisol from baseline in all treatment groups (14%, 22%, and 13% for ADVAIR HFA, ADVAIR HFA with spacer, and ADVAIR DISKUS, respectively).

Other Fluticasone Propionate Products

Subjects with Asthma: Hypothalamic-Pituitary-Adrenal Axis Effects: In clinical trials with fluticasone propionate inhalation powder using dosages up to and including 250 mcg twice daily, occasional abnormal short cosyntropin tests (peak serum cortisol <18 mcg/dL assessed by radioimmunoassay) were noted both in subjects receiving fluticasone propionate and in subjects receiving placebo. The incidence of abnormal tests at 500 mcg twice daily was greater than placebo. In a 2-year trial carried out with the DISKHALER inhalation device in 64 subjects with mild, persistent asthma (mean FEV1 91% of predicted) randomized to fluticasone propionate 500 mcg twice daily or placebo, no subject receiving fluticasone propionate had an abnormal response to 6-hour cosyntropin infusion (peak serum cortisol <18 mcg/dL). With a peak cortisol threshold of <35 mcg/dL, 1 subject receiving fluticasone propionate (4%) had an abnormal response at 1 year; repeat testing at 18 months and 2 years was normal. Another subject receiving fluticasone propionate (5%) had an abnormal response at 2 years. No subject on placebo had an abnormal response at 1 or 2 years.

Other Salmeterol Xinafoate Products

Subjects with Asthma: Cardiovascular Effects: Inhaled salmeterol, like other beta-adrenergic agonist drugs, can produce dose-related cardiovascular effects and effects on blood glucose and/or serum potassium [see Warnings and Precautions (5.12, 5.18)]. The cardiovascular effects (heart rate, blood pressure) associated with salmeterol inhalation aerosol occur with similar frequency, and are of similar type and severity, as those noted following albuterol administration.

The effects of rising inhaled doses of salmeterol and standard inhaled doses of albuterol were studied in volunteers and in subjects with asthma. Salmeterol doses up to 84 mcg administered as inhalation aerosol resulted in heart rate increases of 3 to 16 beats/min, about the same as albuterol dosed at 180 mcg by inhalation aerosol (4 to 10 beats/min). In 2 double‑blind asthma trials, subjects receiving either 42 mcg of salmeterol inhalation aerosol twice daily (n = 81) or 180 mcg of albuterol inhalation aerosol 4 times daily (n = 80) underwent continuous electrocardiographic monitoring during four 24-hour periods; no clinically significant dysrhythmias were noted.

Concomitant Use of ADVAIR HFA with Other Respiratory Medicines

Short-acting Beta2-agonists: In three 12-week U.S. clinical trials, the mean daily need for additional beta2-agonist use in 277 subjects receiving ADVAIR HFA was approximately 1.2 inhalations/day and ranged from 0 to 9 inhalations/day. Two percent (2%) of subjects receiving ADVAIR HFA in these trials averaged 6 or more inhalations per day over the course of the 12-week trials. No increase in frequency of cardiovascular adverse events was observed among subjects who averaged 6 or more inhalations per day.

Methylxanthines: The concurrent use of intravenously or orally administered methylxanthines (e.g., aminophylline, theophylline) by subjects receiving ADVAIR HFA has not been completely evaluated. In five 12-week clinical trials (3 U.S. and 2 non-U.S.), 45 subjects receiving ADVAIR HFA 45 mcg/21 mcg, ADVAIR HFA 115 mcg/21 mcg, or ADVAIR HFA 230 mcg/21 mcg twice daily concurrently with a theophylline product had adverse event rates similar to those in 577 subjects receiving ADVAIR HFA without theophylline.

Fluticasone Propionate Nasal Spray: In subjects receiving ADVAIR HFA in three 12-week U.S. clinical trials, no difference in the profile of adverse events or HPA axis effects was noted between subjects receiving FLONASE (fluticasone propionate) Nasal Spray, 50 mcg concurrently (n = 89) and those who were not (n = 192).

12.3 Pharmacokinetics

Absorption

Fluticasone Propionate: Healthy Subjects: Fluticasone propionate acts locally in the lung; therefore, plasma levels do not predict therapeutic effect. Trials using oral dosing of labeled and unlabeled drug have demonstrated that the oral systemic bioavailability of fluticasone propionate is negligible (<1%), primarily due to incomplete absorption and presystemic metabolism in the gut and liver. In contrast, the majority of the fluticasone propionate delivered to the lung is systemically absorbed.

Three (3) single-dose, placebo-controlled, crossover trials were conducted in healthy subjects: (1) a trial using 4 inhalations of ADVAIR HFA 230 mcg/21 mcg, salmeterol CFC inhalation aerosol 21 mcg, or fluticasone propionate CFC inhalation aerosol 220 mcg, (2) a trial using 8 inhalations of ADVAIR HFA 45 mcg/21 mcg, ADVAIR HFA 115 mcg/21 mcg, or ADVAIR HFA 230 mcg/21 mcg, and (3) a trial using 4 inhalations of ADVAIR HFA 230 mcg/21 mcg; 2 inhalations of ADVAIR DISKUS 500 mcg/50 mcg; 4 inhalations of fluticasone propionate CFC inhalation aerosol 220 mcg; or 1,010 mcg of fluticasone propionate given intravenously. Peak plasma concentrations of fluticasone propionate were achieved in 0.33 to 1.5 hours and those of salmeterol were achieved in 5 to 10 minutes.

Peak plasma concentrations of fluticasone propionate (N = 20 subjects) following 8 inhalations of ADVAIR HFA 45 mcg/21 mcg, ADVAIR HFA 115 mcg/21 mcg, and ADVAIR HFA 230 mcg/21 mcg averaged 41, 108, and 173 pg/mL, respectively.

Systemic exposure (N = 20 subjects) from 4 inhalations of ADVAIR HFA 230 mcg/21 mcg was 53% of the value from the individual inhaler for fluticasone propionate CFC inhalation aerosol and 42% of the value from the individual inhaler for salmeterol CFC inhalation aerosol. Peak plasma concentrations from ADVAIR HFA for fluticasone propionate (86 versus 120 pg/mL) and salmeterol (170 versus 510 pg/mL) were significantly lower compared with individual inhalers.

In 15 healthy subjects, systemic exposure to fluticasone propionate from 4 inhalations of ADVAIR HFA 230 mcg/21 mcg (920/84 mcg) and 2 inhalations of ADVAIR DISKUS 500 mcg/50 mcg (1,000/100 mcg) was similar between the 2 inhalers (i.e., 799 versus 832 pg•h/mL, respectively), but approximately half the systemic exposure from 4 inhalations of fluticasone propionate CFC inhalation aerosol 220 mcg (880 mcg, AUC = 1,543 pg•h/mL). Similar results were observed for peak fluticasone propionate plasma concentrations (186 and 182 pg/mL from ADVAIR HFA and ADVAIR DISKUS, respectively, and 307 pg/mL from the fluticasone propionate CFC inhalation aerosol). Absolute bioavailability of fluticasone propionate was 5.3% and 5.5% following administration of ADVAIR HFA and ADVAIR DISKUS, respectively.

Subjects with Asthma: A double-blind crossover trial was conducted in 13 adult subjects with asthma to evaluate the steady-state pharmacokinetics of fluticasone propionate and salmeterol following administration of 2 inhalations of ADVAIR HFA 115 mcg/21 mcg twice daily or 1 inhalation of ADVAIR DISKUS 250 mcg/50 mcg twice daily for 4 weeks. Systemic exposure (AUC) to fluticasone propionate was similar for ADVAIR HFA (274 pg•h/mL [95% CI: 150, 502]) and ADVAIR DISKUS (338 pg•h/mL [95% CI: 197, 581]).

The effect of 21 days of treatment with ADVAIR HFA 45 mcg/21 mcg (2 inhalations twice daily with or without a spacer) or ADVAIR DISKUS 100 mcg/50 mcg (1 inhalation twice daily) was evaluated in a trial of 31 children aged 4 to 11 years with mild asthma. Systemic exposure to fluticasone propionate was similar with ADVAIR DISKUS and ADVAIR HFA with a spacer (138 pg•h/mL [95% CI: 69, 273] and 107 pg•h/mL [95% CI: 46, 252], respectively) and lower with ADVAIR HFA without a spacer (24 pg•h/mL [95% CI: 10, 60]).

Salmeterol Xinafoate: Healthy Subjects: Salmeterol xinafoate, an ionic salt, dissociates in solution so that the salmeterol and 1-hydroxy-2-naphthoic acid (xinafoate) moieties are absorbed, distributed, metabolized, and eliminated independently. Salmeterol acts locally in the lung; therefore, plasma levels do not predict therapeutic effect.

Peak plasma concentrations of salmeterol (N = 20 subjects) following 8 inhalations of ADVAIR HFA 45 mcg/21 mcg, ADVAIR HFA 115 mcg/21 mcg, and ADVAIR HFA 230 mcg/21 mcg ranged from 220 to 470 pg/mL.

In 15 healthy subjects receiving ADVAIR HFA 230 mcg/21 mcg (920/84 mcg) and ADVAIR DISKUS 500 mcg/50 mcg (1,000/100 mcg), systemic exposure to salmeterol was higher (317 versus 169 pg•h/mL) and peak salmeterol concentrations were lower (196 versus 223 pg/mL) following ADVAIR HFA compared with ADVAIR DISKUS, although pharmacodynamic results were comparable.

Subjects with Asthma: Because of the small therapeutic dose, systemic levels of salmeterol are low or undetectable after inhalation of recommended dosages (42 mcg of salmeterol inhalation aerosol twice daily). Following chronic administration of an inhaled dose of 42 mcg of salmeterol inhalation aerosol twice daily, salmeterol was detected in plasma within 5 to 10 minutes in 6 subjects with asthma; plasma concentrations were very low, with mean peak concentrations of 150 pg/mL at 20 minutes and no accumulation with repeated doses.

A double-blind crossover trial was conducted in 13 adult subjects with asthma to evaluate the steady-state pharmacokinetics of fluticasone propionate and salmeterol following administration of 2 inhalations of ADVAIR HFA 115 mcg/21 mcg twice daily or 1 inhalation of ADVAIR DISKUS 250 mcg/50 mcg twice daily for 4 weeks. Systemic exposure to salmeterol was similar for ADVAIR HFA (53 pg•h/mL [95% CI: 17, 164]) and ADVAIR DISKUS (70 pg•h/mL [95% CI: 19, 254]).

The effect of 21 days of treatment with ADVAIR HFA 45 mcg/21 mcg (2 inhalations twice daily with or without a spacer) or ADVAIR DISKUS 100 mcg/50 mcg (1 inhalation twice daily) was evaluated in 31 children aged 4 to 11 years with mild asthma. Systemic exposure to salmeterol was similar for ADVAIR HFA, ADVAIR HFA with spacer, and ADVAIR DISKUS (126 pg•h/mL [95% CI: 70, 225], 103 pg•h/mL [95% CI: 54, 200], and 110 pg•h/mL [95% CI: 55, 219], respectively).

Distribution

Fluticasone Propionate: Following intravenous administration, the initial disposition phase for fluticasone propionate was rapid and consistent with its high lipid solubility and tissue binding. The volume of distribution averaged 4.2 L/kg.

The percentage of fluticasone propionate bound to human plasma proteins averages 99%. Fluticasone propionate is weakly and reversibly bound to erythrocytes and is not significantly bound to human transcortin.

Salmeterol: The percentage of salmeterol bound to human plasma proteins averages 96% in vitro over the concentration range of 8 to 7,722 ng of salmeterol base per milliliter, much higher concentrations than those achieved following therapeutic doses of salmeterol.

Elimination

Fluticasone Propionate: Following intravenous dosing, fluticasone propionate showed polyexponential kinetics and had a terminal elimination half-life of approximately 7.8 hours. The total clearance of fluticasone propionate is high (average, 1,093 mL/min), with renal clearance accounting for <0.02% of the total. Less than 5% of a radiolabeled oral dose was excreted in the urine as metabolites, with the remainder excreted in the feces as parent drug and metabolites. Terminal half-life estimates of fluticasone propionate for ADVAIR HFA, ADVAIR DISKUS, and fluticasone propionate CFC inhalation aerosol were similar and averaged 5.6 hours.

Salmeterol: In 2 healthy adult subjects who received 1 mg of radiolabeled salmeterol (as salmeterol xinafoate) orally, approximately 25% and 60% of the radiolabeled salmeterol was eliminated in urine and feces, respectively, over a period of 7 days. The terminal elimination half-life was about 5.5 hours (1 volunteer only).

The xinafoate moiety has no apparent pharmacologic activity. The xinafoate moiety is highly protein bound (>99%) and has a long elimination half-life of 11 days. No terminal half-life estimates were calculated for salmeterol following administration of ADVAIR HFA.

Metabolism: Fluticasone Propionate: The only circulating metabolite detected in man is the 17β-carboxylic acid derivative of fluticasone propionate, which is formed through the CYP3A4 pathway. This metabolite had less affinity (approximately 1/2,000) than the parent drug for the glucocorticoid receptor of human lung cytosol in vitro and negligible pharmacological activity in animal studies. Other metabolites detected in vitro using cultured human hepatoma cells have not been detected in man.

Salmeterol: Salmeterol base is extensively metabolized by hydroxylation, with subsequent elimination predominantly in the feces. No significant amount of unchanged salmeterol base was detected in either urine or feces.

An in vitro study using human liver microsomes showed that salmeterol is extensively metabolized to α-hydroxysalmeterol (aliphatic oxidation) by CYP3A4. Ketoconazole, a strong inhibitor of CYP3A4, essentially completely inhibited the formation of α-hydroxysalmeterol in vitro.

Specific Populations

A population pharmacokinetic analysis was performed for fluticasone propionate and salmeterol utilizing data from 9 controlled clinical trials that included 350 subjects with asthma aged 4 to 77 years who received treatment with ADVAIR DISKUS, ADVAIR HFA, fluticasone propionate inhalation powder (FLOVENT DISKUS), HFA-propelled fluticasone propionate inhalation aerosol (FLOVENT HFA), or CFC-propelled fluticasone propionate inhalation aerosol. The population pharmacokinetic analyses for fluticasone propionate and salmeterol showed no clinically relevant effects of age, gender, race, body weight, body mass index, or percent of predicted FEV1 on apparent clearance and apparent volume of distribution.

Patients with Hepatic and Renal Impairment: Formal pharmacokinetic studies using ADVAIR HFA have not been conducted in patients with hepatic or renal impairment. However, since both fluticasone propionate and salmeterol are predominantly cleared by hepatic metabolism, impairment of liver function may lead to accumulation of fluticasone propionate and salmeterol in plasma. Therefore, patients with hepatic disease should be closely monitored.

Drug Interaction Studies

In the repeat- and single-dose trials, there was no evidence of significant drug interaction in systemic exposure between fluticasone propionate and salmeterol when given alone or in combination via the DISKUS. Similar definitive studies have not been performed with ADVAIR HFA. The population pharmacokinetic analysis from 9 controlled clinical trials in 350 subjects with asthma showed no significant effects on fluticasone propionate or salmeterol pharmacokinetics following co-administration with beta2-agonists, corticosteroids, antihistamines, or theophyllines.

Inhibitors of Cytochrome P450 3A4: Ritonavir: Fluticasone Propionate: Fluticasone propionate is a substrate of CYP3A4. Coadministration of fluticasone propionate and the strong CYP3A4 inhibitor ritonavir is not recommended based upon a multiple-dose, crossover drug interaction trial in 18 healthy subjects. Fluticasone propionate aqueous nasal spray (200 mcg once daily) was coadministered for 7 days with ritonavir (100 mg twice daily). Plasma fluticasone propionate concentrations following fluticasone propionate aqueous nasal spray alone were undetectable (<10 pg/mL) in most subjects, and when concentrations were detectable peak levels (Cmax) averaged 11.9 pg/mL (range: 10.8 to 14.1 pg/mL) and AUC(0-τ) averaged 8.43 pg•h/mL (range: 4.2 to 18.8 pg•h/mL). Fluticasone propionate Cmax and AUC(0-τ) increased to 318 pg/mL (range: 110 to 648 pg/mL) and 3,102.6 pg•h/mL (range: 1,207.1 to 5,662.0 pg•h/mL), respectively, after coadministration of ritonavir with fluticasone propionate aqueous nasal spray. This significant increase in plasma fluticasone propionate exposure resulted in a significant decrease (86%) in serum cortisol AUC.

Ketoconazole: Fluticasone Propionate: In a placebo-controlled crossover trial in 8 healthy adult volunteers, coadministration of a single dose of orally inhaled fluticasone propionate (1,000 mcg) with multiple doses of ketoconazole (200 mg) to steady state resulted in increased plasma fluticasone propionate exposure, a reduction in plasma cortisol AUC, and no effect on urinary excretion of cortisol.

Salmeterol: In a placebo-controlled, crossover drug interaction trial in 20 healthy male and female subjects, coadministration of salmeterol (50 mcg twice daily) and the strong CYP3A4 inhibitor ketoconazole (400 mg once daily) for 7 days resulted in a significant increase in plasma salmeterol exposure as determined by a 16-fold increase in AUC (ratio with and without ketoconazole 15.76 [90% CI: 10.66, 23.31]) mainly due to increased bioavailability of the swallowed portion of the dose. Peak plasma salmeterol concentrations were increased by 1.4-fold (90% CI: 1.23, 1.68). Three (3) out of 20 subjects (15%) were withdrawn from salmeterol and ketoconazole coadministration due to beta-agonist–mediated systemic effects (2 with QTc prolongation and 1 with palpitations and sinus tachycardia). Coadministration of salmeterol and ketoconazole did not result in a clinically significant effect on mean heart rate, mean blood potassium, or mean blood glucose. Although there was no statistical effect on the mean QTc, coadministration of salmeterol and ketoconazole was associated with more frequent increases in QTc duration compared with salmeterol and placebo administration.

Erythromycin: Fluticasone Propionate: In a multiple-dose drug interaction trial, coadministration of orally inhaled fluticasone propionate (500 mcg twice daily) and erythromycin (333 mg 3 times daily) did not affect fluticasone propionate pharmacokinetics.

Salmeterol: In a repeat-dose trial in 13 healthy subjects, concomitant administration of erythromycin (a moderate CYP3A4 inhibitor) and salmeterol inhalation aerosol resulted in a 40% increase in salmeterol Cmax at steady state (ratio with and without erythromycin 1.4 [90% CI: 0.96, 2.03], P = 0.12), a 3.6-beat/min increase in heart rate ([95% CI: 0.19, 7.03], P<0.04), a 5.8-msec increase in QTc interval ([95% CI: -6.14, 17.77], P = 0.34), and no change in plasma potassium.

13 NONCLINICAL TOXICOLOGY

13.1 Carcinogenesis, Mutagenesis, Impairment of Fertility

Fluticasone Propionate

Fluticasone propionate demonstrated no tumorigenic potential in mice at oral doses up to 1,000 mcg/kg (approximately 5 times the MRHDID on a mcg/m^2 basis) for 78 weeks or in rats at inhalation doses up to 57 mcg/kg (approximately 0.5 times the MRHDID on a mcg/m^2 basis) for 104 weeks.

Fluticasone propionate did not induce gene mutation in prokaryotic or eukaryotic cells in vitro. No significant clastogenic effect was seen in cultured human peripheral lymphocytes in vitro or in the in vivo mouse micronucleus test.

Fertility and reproductive performance were unaffected in male and female rats at subcutaneous doses up to 50 mcg/kg (approximately 0.5 times the MRHDID for adults on a mcg/m^2 basis).

Salmeterol

In an 18-month carcinogenicity study in CD-mice, salmeterol at oral doses of 1,400 mcg/kg and above (approximately 10 times the MRHDID based on comparison of the plasma AUCs) caused a dose-related increase in the incidence of smooth muscle hyperplasia, cystic glandular hyperplasia, leiomyomas of the uterus, and ovarian cysts. No tumors were seen at 200 mcg/kg (approximately 2 times the MRHDID for adults based on comparison of the AUCs).

In a 24-month oral and inhalation carcinogenicity study in Sprague Dawley rats, salmeterol caused a dose-related increase in the incidence of mesovarian leiomyomas and ovarian cysts at doses of 680 mcg/kg and above (approximately 80 times the MRHDID on a mcg/m^2 basis). No tumors were seen at 210 mcg/kg (approximately 25 times the MRHDID on a mcg/m^2 basis). These findings in rodents are similar to those reported previously for other beta-adrenergic agonist drugs. The relevance of these findings to human use is unknown.

Salmeterol produced no detectable or reproducible increases in microbial and mammalian gene mutation in vitro. No clastogenic activity occurred in vitro in human lymphocytes or in vivo in a rat micronucleus test.

Fertility and reproductive performance were unaffected in male and female rats at oral doses up to 2,000 mcg/kg (approximately 230 times the MRHDID for adults on a mcg/m^2 basis).

13.2 Animal Toxicology and/or Pharmacology

Studies in laboratory animals (minipigs, rodents, and dogs) have demonstrated the occurrence of cardiac arrhythmias and sudden death (with histologic evidence of myocardial necrosis) when beta-agonists and methylxanthines are administered concurrently. The clinical relevance of these findings is unknown.

14 CLINICAL STUDIES

ADVAIR HFA has been studied in subjects with asthma aged 12 years and older. ADVAIR HFA has not been studied in subjects younger than 12 years or in subjects with COPD. In clinical trials comparing ADVAIR HFA with its individual components, improvements in most efficacy endpoints were greater with ADVAIR HFA than with the use of either fluticasone propionate or salmeterol alone. In addition, clinical trials showed comparable results between ADVAIR HFA and ADVAIR DISKUS.

14.1 Trials Comparing ADVAIR HFA with Fluticasone Propionate Alone or Salmeterol Alone

Four (4) double-blind, parallel-group clinical trials were conducted with ADVAIR HFA in 1,517 adult and adolescent subjects (aged 12 years and older, mean baseline FEV1 65% to 75% of predicted normal) with asthma that was not optimally controlled on their current therapy. All metered-dose inhaler treatments were inhalation aerosols given as 2 inhalations twice daily, and other maintenance therapies were discontinued.

Trial 1: Clinical Trial with ADVAIR HFA 45 mcg/21 mcg

This placebo-controlled, 12-week, U.S. trial compared ADVAIR HFA 45 mcg/21 mcg with fluticasone propionate CFC inhalation aerosol 44 mcg or salmeterol CFC inhalation aerosol 21 mcg, each given as 2 inhalations twice daily. The primary efficacy endpoints were predose FEV1 and withdrawals due to worsening asthma. This trial was stratified according to baseline asthma therapy: subjects using beta-agonists (albuterol alone [n = 142], salmeterol [n = 84], or ICS [n = 134] [daily doses of beclomethasone dipropionate 252 to 336 mcg; budesonide 400 to 600 mcg; flunisolide 1,000 mcg; fluticasone propionate inhalation aerosol 176 mcg; fluticasone propionate inhalation powder 200 mcg; or triamcinolone acetonide 600 to 800 mcg]). Baseline FEV1 measurements were similar across treatments: ADVAIR HFA 45 mcg/21 mcg, 2.29 L; fluticasone propionate 44 mcg, 2.20 L; salmeterol, 2.33 L; and placebo, 2.27 L.

Predefined withdrawal criteria for lack of efficacy, an indicator of worsening asthma, were utilized for this placebo-controlled trial. Worsening asthma was defined as a clinically important decrease in FEV1 or PEF, increase in use of VENTOLIN (albuterol, USP) Inhalation Aerosol, increase in night awakenings due to asthma, emergency intervention or hospitalization due to asthma, or requirement for asthma medicine not allowed by the protocol. As shown in Table 3, statistically significantly fewer subjects receiving ADVAIR HFA 45 mcg/21 mcg were withdrawn due to worsening asthma compared with salmeterol and placebo. Fewer subjects receiving ADVAIR HFA 45 mcg/21 mcg were withdrawn due to worsening asthma compared with fluticasone propionate 44 mcg; however, the difference was not statistically significant.

Table 3. Percent of Subjects Withdrawn due to Worsening Asthma in Subjects Previously Treated with Beta2-agonists (Albuterol or Salmeterol) or Inhaled Corticosteroids (Trial 1)
ADVAIR HFA 45 mcg/21 mcg; (n = 92) | Fluticasone Propionate CFC Inhalation Aerosol; 44 mcg; (n = 89) | Salmeterol CFC Inhalation Aerosol; 21 mcg; (n = 92) | Placebo HFA Inhalation Aerosol; (n = 87)
2% | 8% | 25% | 28%

The FEV1 results are displayed in Figure 1. Because this trial used predetermined criteria for worsening asthma, which caused more subjects in the placebo group to be withdrawn, FEV1 results at Endpoint (last available FEV1 result) are also provided. Subjects receiving ADVAIR HFA 45 mcg/21 mcg had significantly greater improvements in FEV1 (0.58 L, 27%) compared with fluticasone propionate 44 mcg (0.36 L, 18%), salmeterol (0.25 L, 12%), and placebo (0.14 L, 5%). These improvements in FEV1 with ADVAIR HFA 45 mcg/21 mcg were achieved regardless of baseline asthma therapy (albuterol alone, salmeterol, or ICS).

Figure 1. Mean Percent Change from Baseline in FEV1 in Subjects Previously Treated with Either Beta2‑agonists (Albuterol or Salmeterol) or Inhaled Corticosteroids (Trial 1)

The effect of ADVAIR HFA 45 mcg/21 mcg on the secondary efficacy parameters, including morning and evening PEF, usage of VENTOLIN Inhalation Aerosol, and asthma symptoms over 24 hours on a scale of 0 to 5 is shown in Table 4.

Table 4. Secondary Efficacy Variable Results for Subjects Previously Treated with Beta2agonists (Albuterol or Salmeterol) or Inhaled Corticosteroids (Trial 1)
Efficacy Variablea | ADVAIR HFA; 45 mcg/21 mcg; (n = 92) | Fluticasone Propionate CFC Inhalation Aerosol; 44 mcg; (n = 89) | Salmeterol CFC Inhalation Aerosol; 21 mcg; (n = 92) | Placebo HFA Inhalation Aerosol; (n = 87)
AM PEF (L/min)
Baseline | 377 | 369 | 381 | 382
Change from baseline | 58 | 27 | 25 | 1
PM PEF (L/min)
Baseline | 397 | 387 | 402 | 407
Change from baseline | 48 | 20 | 16 | 3
Use of VENTOLIN Inhalation Aerosol (inhalations/day)
Baseline | 3.1 | 2.4 | 2.7 | 2.7
Change from baseline | -2.1 | -0.4 | -0.8 | 0.2
Asthma symptom score/day
Baseline | 1.8 | 1.6 | 1.7 | 1.7
Change from baseline | -1.0 | -0.3 | -0.4 | 0
a Change from baseline = change from baseline at Endpoint (last available data).

The subjective impact of asthma on subjects’ perception of health was evaluated through use of an instrument called the Asthma Quality of Life Questionnaire (AQLQ) (based on a 7-point scale where 1 = maximum impairment and 7 = none). Subjects receiving ADVAIR HFA 45 mcg/21 mcg had clinically meaningful improvements in overall asthma-specific quality of life as defined by a difference between groups of ≥0.5 points in change from baseline AQLQ scores (difference in AQLQ score of 1.14 [95% CI: 0.85, 1.44] compared with placebo).

Trial 2: Clinical Trial with ADVAIR HFA 45 mcg/21 mcg

This active-controlled, 12-week, U.S. trial compared ADVAIR HFA 45 mcg/21 mcg with fluticasone propionate CFC inhalation aerosol 44 mcg and salmeterol CFC inhalation aerosol 21 mcg, each given as 2 inhalations twice daily, in 283 subjects using as-needed albuterol alone. The primary efficacy endpoint was predose FEV1. Baseline FEV1 measurements were similar across treatments: ADVAIR HFA 45 mcg/21 mcg, 2.37 L; fluticasone propionate 44 mcg, 2.31 L; and salmeterol, 2.34 L.

Efficacy results in this trial were similar to those observed in Trial 1. Subjects receiving ADVAIR HFA 45 mcg/21 mcg had significantly greater improvements in FEV1 (0.69 L, 33%) compared with fluticasone propionate 44 mcg (0.51 L, 25%) and salmeterol (0.47 L, 22%).

Trial 3: Clinical Trial with ADVAIR HFA 115 mcg/21 mcg

This placebo-controlled, 12-week, U.S. trial compared ADVAIR HFA 115 mcg/21 mcg with fluticasone propionate CFC inhalation aerosol 110 mcg or salmeterol CFC inhalation aerosol 21 mcg, each given as 2 inhalations twice daily, in 365 subjects using ICS (daily doses of beclomethasone dipropionate 378 to 840 mcg; budesonide 800 to 1,200 mcg; flunisolide 1,250 to 2,000 mcg; fluticasone propionate inhalation aerosol 440 to 660 mcg; fluticasone propionate inhalation powder 400 to 600 mcg; or triamcinolone acetonide 900 to 1,600 mcg). The primary efficacy endpoints were predose FEV1 and withdrawals due to worsening asthma. Baseline FEV1 measurements were similar across treatments: ADVAIR HFA 115 mcg/21 mcg, 2.23 L; fluticasone propionate 110 mcg, 2.18 L; salmeterol, 2.22 L; and placebo, 2.17 L.

Efficacy results in this trial were similar to those observed in Trials 1 and 2. Subjects receiving ADVAIR HFA 115 mcg/21 mcg had significantly greater improvements in FEV1 (0.41 L, 20%) compared with fluticasone propionate 110 mcg (0.19 L, 9%), salmeterol (0.15 L, 8%), and placebo (-0.12 L, -6%). Significantly fewer subjects receiving ADVAIR HFA 115 mcg/21 mcg were withdrawn from this trial for worsening asthma (7%) compared with salmeterol (24%) and placebo (54%). Fewer subjects receiving ADVAIR HFA 115 mcg/21 mcg were withdrawn due to worsening asthma (7%) compared with fluticasone propionate 110 mcg (11%); however, the difference was not statistically significant.

Trial 4: Clinical Trial with ADVAIR HFA 230 mcg/21 mcg

This active-controlled, 12-week, non-U.S. trial compared ADVAIR HFA 230 mcg/21 mcg with fluticasone propionate CFC inhalation aerosol 220 mcg, each given as 2 inhalations twice daily, and with ADVAIR DISKUS 500 mcg /50 mcg given as 1 inhalation twice daily in 509 subjects using ICS (daily doses of beclomethasone dipropionate CFC inhalation aerosol 1,500 to 2,000 mcg; budesonide 1,500 to 2,000 mcg; flunisolide 1,500 to 2,000 mcg; fluticasone propionate inhalation aerosol 660 to 880 mcg; or fluticasone propionate inhalation powder 750 to 1,000 mcg). The primary efficacy endpoint was morning PEF.

Baseline morning PEF measurements were similar across treatments: ADVAIR HFA 230 mcg/21 mcg, 327 L/min; ADVAIR DISKUS 500 mcg/50 mcg, 341 L/min; and fluticasone propionate 220 mcg, 345 L/min. As shown in Figure 2, morning PEF improved significantly with ADVAIR HFA 230 mcg/21 mcg compared with fluticasone propionate 220 mcg over the 12-week treatment period. Improvements in morning PEF observed with ADVAIR HFA 230 mcg/21 mcg were similar to improvements observed with ADVAIR DISKUS 500 mcg/50 mcg.

Figure 2. Mean Percent Change from Baseline in Morning Peak Expiratory Flow in Subjects Previously Treated with Inhaled Corticosteroids (Trial 4)

14.2 One-Year Safety Trial

Clinical Trial with ADVAIR HFA 45 mcg/21 mcg, ADVAIR HFA 115 mcg/21 mcg, and ADVAIR HFA 230 mcg/21 mcg

This 1-year, open-label, non-U.S. trial evaluated the safety of ADVAIR HFA 45 mcg/21 mcg, ADVAIR HFA 115 mcg/21 mcg, and ADVAIR HFA 230 mcg/21 mcg given as 2 inhalations twice daily in 325 subjects. This trial was stratified into 3 groups according to baseline asthma therapy: subjects using short-acting beta2-agonists alone (n = 42), salmeterol (n = 91), or ICS (n = 277). Subjects treated with short-acting beta2-agonists alone, salmeterol, or low doses of ICS with or without concurrent salmeterol received ADVAIR HFA 45 mcg/21 mcg. Subjects treated with moderate doses of ICS with or without concurrent salmeterol received ADVAIR HFA 115 mcg/21 mcg. Subjects treated with high doses of ICS with or without concurrent salmeterol received ADVAIR HFA 230 mcg/21 mcg. Baseline FEV1 measurements ranged from 2.3 to 2.6 L.

Improvements in FEV1 (0.17 to 0.35 L at 4 weeks) were seen across all 3 treatments and were sustained throughout the 52-week treatment period. Few subjects (3%) were withdrawn due to worsening asthma over 1 year.

14.3 Onset of Action and Progression of Improvement in Control

The onset of action and progression of improvement in asthma control were evaluated in 2 placebo-controlled U.S. trials and 1 active-controlled U.S. trial. Following the first dose, the median time to onset of clinically significant bronchodilatation (≥15% improvement in FEV1) in most subjects was seen within 30 to 60 minutes. Maximum improvement in FEV1 occurred within 4 hours, and clinically significant improvement was maintained for 12 hours (Figure 3).

Following the initial dose, predose FEV1 relative to Day 1 baseline improved markedly over the first week of treatment and continued to improve over the 12 weeks of treatment in all 3 trials.

No diminution in the 12-hour bronchodilator effect was observed with either ADVAIR HFA 45 mcg/21 mcg (Figures 3 and 4) or ADVAIR HFA 230/21 as assessed by FEV1 following 12 weeks of therapy.

Figure 3. Percent Change in Serial 12-Hour FEV1 in Subjects Previously Using Either Beta2-agonists (Albuterol or Salmeterol) or Inhaled Corticosteroids (Trial 1)

First Treatment Day

Figure 4. Percent Change in Serial 12-Hour FEV1 in Subjects Previously Using Either Beta2-agonists (Albuterol or Salmeterol) or Inhaled Corticosteroids (Trial 1)

Last Treatment Day (Week 12)

Reduction in asthma symptoms and use of rescue VENTOLIN Inhalation Aerosol and improvement in morning and evening PEF also occurred within the first day of treatment with ADVAIR HFA and continued to improve over the 12 weeks of therapy in all 3 trials.

16 HOW SUPPLIED/STORAGE AND HANDLING

Product: 50090-4504

NDC: 50090-4504-0 120 AEROSOL, METERED in a INHALER / 1 in a CARTON

17 PATIENT COUNSELING INFORMATION

Advise the patient to read the FDA-approved patient labeling (Patient Information and Instructions for Use).

Serious Asthma-Related Events

Inform patients with asthma that LABA when used alone increases the risk of asthma-related hospitalization or asthma-related death. Available data show that when ICS and LABA are used together, such as with ADVAIR HFA, there is not a significant increase in the risk of these events. [See Warnings and Precautions (5.1).]

Not for Acute Symptoms

Inform patients that ADVAIR HFA is not meant to relieve acute asthma symptoms and extra doses should not be used for that purpose. Advise patients to treat acute asthma symptoms with an inhaled, short-acting beta2-agonist such as albuterol. Provide patients with such medication and instruct them in how it should be used.

Instruct patients to seek medical attention immediately if they experience any of the following:

- Decreasing effectiveness of inhaled, short-acting beta2-agonists
- Need for more inhalations than usual of inhaled, short-acting beta2-agonists
- Significant decrease in lung function as outlined by the physician

Tell patients they should not stop therapy with ADVAIR HFA without physician/provider guidance since symptoms may recur after discontinuation. [See Warnings and Precautions (5.2).]

Do Not Use Additional Long-acting Beta2-agonists

Instruct patients not to use other LABA for asthma. [See Warnings and Precautions (5.3).]

Oropharyngeal Candidiasis

Inform patients that localized infections with Candida albicans occurred in the mouth and pharynx in some patients. If oropharyngeal candidiasis develops, treat it with appropriate local or systemic (i.e., oral) antifungal therapy while still continuing therapy with ADVAIR HFA, but at times therapy with ADVAIR HFA may need to be temporarily interrupted under close medical supervision. Advise patients to rinse the mouth with water without swallowing after inhalation to help reduce the risk of thrush. [See Warnings and Precautions (5.4).]

Pneumonia

Patients with COPD have a higher risk of pneumonia; instruct them to contact their healthcare providers if they develop symptoms of pneumonia. [See Warnings and Precautions (5.5).]

Immunosuppression and Risk of Infections

Warn patients who are on immunosuppressant doses of corticosteroids to avoid exposure to chickenpox or measles and, if exposed, to consult their physicians without delay. Inform patients of potential worsening of existing tuberculosis; fungal, bacterial, viral, or parasitic infections; or ocular herpes simplex. [See Warnings and Precautions (5.6).]

Hypercorticism and Adrenal Suppression

Advise patients that ADVAIR HFA may cause systemic corticosteroid effects of hypercorticism and adrenal suppression. Additionally, inform patients that deaths due to adrenal insufficiency have occurred during and after transfer from systemic corticosteroids. Patients should taper slowly from systemic corticosteroids if transferring to ADVAIR HFA. [See Warnings and Precautions (5.8).]

Hypersensitivity Reactions, including Anaphylaxis

Advise patients that immediate hypersensitivity reactions (e.g., urticaria, angioedema, rash, bronchospasm, hypotension), including anaphylaxis, may occur after administration of ADVAIR HFA. Patients should discontinue ADVAIR HFA if such reactions occur. [See Warnings and Precautions (5.11).]

Risks Associated with Beta-agonist Therapy

Inform patients of adverse effects associated with beta2-agonists, such as palpitations, chest pain, rapid heart rate, tremor, or nervousness. [See Warnings and Precautions (5.12).]

Reduction in Bone Mineral Density

Advise patients who are at an increased risk for decreased BMD that the use of corticosteroids may pose an additional risk. [See Warnings and Precautions (5.13).]

Reduced Growth Velocity

Inform patients that orally inhaled corticosteroids, including fluticasone propionate, may cause a reduction in growth velocity when administered to pediatric patients. Physicians should closely follow the growth of children and adolescents taking corticosteroids by any route. [See Warnings and Precautions (5.14).]

Glaucoma and Cataracts

Advise patients that long-term use of ICS may increase the risk of some eye problems (cataracts or glaucoma); consider regular eye examinations. [See Warnings and Precautions (5.15).]

Trademarks are owned by or licensed to the GSK group of companies.

GlaxoSmithKline

Durham, NC 27701

©2024 GSK group of companies or its licensor.

ADH:19PI

PATIENT INFORMATION

ADVAIR (AD vair) HFA

(fluticasone propionate and salmeterol inhalation aerosol)

for oral inhalation use

What is ADVAIR HFA?

- ADVAIR HFA combines the inhaled corticosteroid (ICS) medicine fluticasone propionate and the long-acting beta2-adrenergic agonist (LABA) medicine salmeterol.
  - ICS medicines such as fluticasone propionate help to decrease inflammation in the lungs. Inflammation in the lungs can lead to breathing problems.
  - LABA medicines such as salmeterol help the muscles around the airways in your lungs stay relaxed to prevent symptoms, such as wheezing, cough, chest tightness, and shortness of breath. These symptoms can happen when the muscles around the airways tighten. This makes it hard to breathe.
- ADVAIR HFA is not used to relieve sudden breathing problems and will not replace a rescue inhaler.
- It is not known if ADVAIR HFA is safe and effective in children younger than 12 years of age.
- ADVAIR HFA is used for asthma as follows:
  - ADVAIR HFA is a prescription medicine used to control symptoms of asthma and to prevent symptoms such as wheezing in adults and adolescents aged 12 years and older.
  - ADVAIR HFA contains salmeterol, the same medicine found in SEREVENT DISKUS (salmeterol xinafoate inhalation powder). LABA medicines such as salmeterol when used alone increase the risk of hospitalizations and death from asthma problems. ADVAIR HFA contains an ICS and a LABA. When an ICS and LABA are used together, there is not a significant increased risk in hospitalizations and death from asthma problems.
  - ADVAIR HFA is not for adults and adolescents with asthma who are well controlled with an asthma control medicine, such as a low to medium dose of an ICS medicine. ADVAIR HFA is for adults and adolescents with asthma who need both an ICS and LABA medicine.

Do not use ADVAIR HFA:

- to relieve sudden breathing problems.
- as a rescue inhaler.
- if you are allergic to fluticasone propionate, salmeterol, or any of the ingredients in ADVAIR HFA. See the end of this Patient Information for a complete list of ingredients in ADVAIR HFA.

Before using ADVAIR HFA, tell your healthcare provider about all of your medical conditions, including if you:

- have heart problems.
- have high blood pressure.
- have seizures.
- have thyroid problems.
- have diabetes.
- have liver problems.
- have weak bones (osteoporosis).
- have an immune system problem.
- have or have had eye problems such as glaucoma, increased pressure in your eye, cataracts, or other changes in vision.
- have any type of viral, bacterial, or fungal infection.
- are exposed to chickenpox or measles.
- are pregnant or plan to become pregnant. It is not known if ADVAIR HFA may harm your unborn baby.
- are breastfeeding. It is not known if the medicines in ADVAIR HFA pass into your milk and if they can harm your baby.

Tell your healthcare provider about all the medicines you take, including prescription and over-the-counter medicines, vitamins, and herbal supplements. ADVAIR HFA and certain other medicines may interact with each other. This may cause serious side effects. Especially tell your healthcare provider if you take antifungal or anti-HIV medicines.

Know the medicines you take. Keep a list of them to show your healthcare provider and pharmacist when you get a new medicine.

How should I use ADVAIR HFA?

Read the step-by-step instructions for using ADVAIR HFA at the end of this Patient Information.

- Do not use ADVAIR HFA unless your healthcare provider has taught you how to use the inhaler and you understand how to use it correctly.
- ADVAIR HFA comes in 3 different strengths. Your healthcare provider prescribed the strength that is best for you.
- Use ADVAIR HFA exactly as your healthcare provider tells you to use it. Do not use ADVAIR HFA more often than prescribed.
- Use 2 inhalations of ADVAIR HFA 2 times each day. Use ADVAIR HFA at the same time each day, about 12 hours apart.
- If you miss a dose of ADVAIR HFA, just skip that dose. Take your next dose at your usual time. Do not take 2 doses at 1 time.
- If you take too much ADVAIR HFA, call your healthcare provider or go to the nearest hospital emergency room right away if you have any unusual symptoms, such as worsening shortness of breath, chest pain, increased heart rate, or shakiness.
- Do not use other medicines that contain a LABA for any reason. Ask your healthcare provider or pharmacist if any of your other medicines are LABA medicines.
- Do not stop using ADVAIR HFA, even if you are feeling better, unless your healthcare provider tells you to.
- ADVAIR HFA does not relieve sudden breathing problems. Always have a rescue inhaler with you to treat sudden symptoms. If you do not have a rescue inhaler, call your healthcare provider to have one prescribed for you.
- Rinse your mouth with water without swallowing after each dose of ADVAIR HFA. This will help lessen the chance of getting a yeast infection (thrush) in your mouth and throat.
- Call your healthcare provider or get medical care right away if:
  - your breathing problems get worse.
  - you need to use your rescue inhaler more often than usual.
  - your rescue inhaler does not work as well to relieve your symptoms.
  - you need to use 4 or more inhalations of your rescue inhaler in 24 hours for 2 or more days in a row.
  - you use 1 whole canister of your rescue inhaler in 8 weeks.
  - your peak flow meter results decrease. Your healthcare provider will tell you the numbers that are right for you.
  - you have asthma and your symptoms do not improve after using ADVAIR HFA regularly for 1 week.

What are the possible side effects of ADVAIR HFA?

ADVAIR HFA can cause serious side effects, including:

- fungal infection in your mouth or throat (thrush). Rinse your mouth with water without swallowing after using ADVAIR HFA to help reduce your chance of getting thrush.
- pneumonia. ADVAIR HFA contains the same medicine found in ADVAIR DISKUS (fluticasone propionate and salmeterol inhalation powder). ADVAIR DISKUS is used to treat people with asthma and people with chronic obstructive pulmonary disease (COPD). People with COPD have a higher chance of getting pneumonia. ADVAIR DISKUS may increase the chance of you getting pneumonia. It is not known if ADVAIR HFA is safe and effective in people with COPD. Call your healthcare provider right away if you have any of the following symptoms:

○increase in mucus (sputum) production
○change in mucus color
○fever

○chills
○increased cough
○increased breathing problems

- weakened immune system and increased chance of getting infections (immunosuppression).
- reduced adrenal function (adrenal insufficiency). Adrenal insufficiency is a condition where the adrenal glands do not make enough steroid hormones. This can happen when you stop taking oral corticosteroid medicines (such as prednisone) and start taking a medicine containing an inhaled steroid (such as ADVAIR HFA). During this transition period, when your body is under stress such as from fever, trauma (such as a car accident), infection, surgery, or worse COPD symptoms, adrenal insufficiency can get worse and may cause death.
Symptoms of adrenal insufficiency include:

○feeling tired
○lack of energy
○weakness

○nausea and vomiting
○low blood pressure (hypotension)

- sudden breathing problems immediately after inhaling your medicine. If you have sudden breathing problems immediately after inhaling your medicine, stop using ADVAIR HFA and call your healthcare provider right away.
- serious allergic reactions. Call your healthcare provider or get emergency medical care if you get any of the following symptoms of a serious allergic reaction:

○rash
○hives

○swelling of your face, mouth, and tongue
○breathing problems

- effects on heart.

○increased blood pressure
○a fast or irregular heartbeat

○chest pain

- effects on nervous system.

○tremor

○nervousness

- bone thinning or weakness (osteoporosis).
- slowed growth in children. Your child’s growth should be checked regularly by the healthcare provider while using ADVAIR HFA.
- eye problems including glaucoma, increased pressure in your eye, cataracts, or other changes in vision. You should have regular eye exams while using ADVAIR HFA.
- changes in laboratory blood levels (sugar, potassium, certain types of white blood cells).

Common side effects of ADVAIR HFA include:

- upper respiratory tract infection
- throat irritation
- hoarseness and voice changes

- headache
- dizziness
- nausea and vomiting

These are not all the possible side effects of ADVAIR HFA.

Call your doctor for medical advice about side effects. You may report side effects to FDA at 1-800-FDA-1088.

How should I store ADVAIR HFA?

- Store ADVAIR HFA at room temperature between 68°F and 77°F (20°C and 25°C) with the mouthpiece down.
- The contents of your ADVAIR HFA are under pressure: Do not puncture. Do not use or store near heat or open flame. Temperatures above 120°F may cause the canister to burst.
- Do not throw into fire or an incinerator.
- Safely throw away ADVAIR HFA in the trash when the counter reads 000.

Keep ADVAIR HFA and all medicines out of the reach of children.

General information about the safe and effective use of ADVAIR HFA.

Medicines are sometimes prescribed for purposes other than those listed in a Patient Information leaflet. Do not use ADVAIR HFA for a condition for which it was not prescribed. Do not give ADVAIR HFA to other people, even if they have the same symptoms that you have. It may harm them.

You can ask your healthcare provider or pharmacist for information about ADVAIR HFA that was written for health professionals.

What are the ingredients in ADVAIR HFA?

Active ingredients: fluticasone propionate, salmeterol xinafoate

Inactive ingredient: propellant HFA-134a

For more information about ADVAIR HFA, call 1-888-825-5249.

Trademarks are owned by or licensed to the GSK group of companies.

GlaxoSmithKline, Durham, NC 27701

©2023 GSK group of companies or its licensor.

ADH:15PIL

This Patient Information has been approved by the U.S. Food and Drug Administration Revised: July 2023

INSTRUCTIONS FOR USE

ADVAIR (AD vair) HFA

(fluticasone propionate and salmeterol inhalation aerosol)

for oral inhalation use

Your ADVAIR HFA inhaler

Figure A

- The metal canister holds the medicine. See Figure A.
- The metal canister has a counter to show how many sprays of medicine you have left. The number shows through a window in the back of the purple plastic actuator. See Figure A.

- The counter starts at either 124 or 064, depending on which size inhaler you have. The number will count down by 1 each time you spray the inhaler. The counter will stop counting at 000.
- Do not try to change the numbers or take the counter off the metal canister. The counter cannot be reset, and it is permanently attached to the metal canister.
- The purple plastic actuator sprays the medicine from the metal canister. The plastic actuator has a light purple protective cap that covers the mouthpiece. See Figure A. Keep the protective cap on the mouthpiece when the metal canister is not in use.
- Do not use the plastic actuator with a canister of medicine from any other inhaler.
- Do not use an ADVAIR HFA metal canister with an actuator from any other inhaler.

Before using your ADVAIR HFA inhaler

- The inhaler should be at room temperature before you use it.

Priming your ADVAIR HFA inhaler

Figure B

Figure C

Figure D

Before you use ADVAIR HFA for the first time, you must prime the inhaler so that you will get the right amount of medicine when you use it.

- To take the cap off the mouthpiece, squeeze the sides of the cap and pull it straight out. See Figure B.
- Shake the inhaler well for 5 seconds.
- Spray the inhaler 1 time into the air away from your face. Avoid spraying in eyes. See Figure C.
- Shake and spray the inhaler like this 3 more times to finish priming it. The counter should now read 120 or 060, depending on which size inhaler you have. See Figure D.
- You must prime your inhaler again if you have not used it in more than 4 weeks or if you have dropped it. To take the cap off the mouthpiece, squeeze the sides of the cap and pull it straight out. Shake the inhaler well for 5 seconds. Then spray it 1 time into the air away from your face. Shake and spray the inhaler like this 1 more time to finish priming it.

How to use your ADVAIR HFA inhaler

Follow these steps every time you use ADVAIR HFA.

Figure E

Figure F

Figure G

Figure H

Step 1. Make sure the metal canister fits firmly in the plastic actuator. The counter should show through the window in the actuator.
To take the cap off the mouthpiece, squeeze the sides of the cap and pull it straight out.
Look inside the mouthpiece for foreign objects and take out any you see.
Step 2. Hold the inhaler with the mouthpiece down and shake it well for 5 seconds . See Figure E.
Step 3. Breathe out through your mouth and push as much air from your lungs as you can. See Figure F.
Step 4. Put the mouthpiece in your mouth and close your lips around it. Push the top of the metal canister firmly all the way down while you breathe in deeply and slowly through your mouth. See Figure G.
Step 5. After the spray comes out, take your finger off the metal canister. After you have breathed in all the way, take the inhaler out of your mouth and close your mouth.
Step 6. Hold your breath for about 10 seconds, or for as long as is comfortable. Breathe out slowly as long as you can.
Wait about 30 seconds and shake the inhaler well for 5 seconds. Repeat Step 2 through Step 6.
Step 7. Rinse your mouth with water after breathing in the medicine. Spit out the water. Do not swallow it. See Figure H.
Step 8. Put the cap back on the mouthpiece after you finish using the inhaler. Make sure it snaps firmly into place.

Cleaning your ADVAIR HFA inhaler

Figure I

Figure J

Clean your inhaler at least 1 time each week after your evening dose. You may not see any medicine build-up on the inhaler, but it is important to keep it clean so medicine build-up will not block the spray. See Figure I.

Step 9. Take the cap off the mouthpiece by squeezing the sides of the cap and pulling it straight out. Do not take the metal canister out of the plastic actuator.
Step 10. Use a dry cotton swab to clean the small circular opening where the medicine sprays out of the canister. Carefully twist the swab in a circular motion to take off any medicine. See Figure J.
Step 11. Wipe the inside of the mouthpiece with a clean tissue dampened with water. Let the plastic actuator air-dry overnight.
Step 12. Put the cap back on the mouthpiece after the plastic actuator has dried.

Replacing your ADVAIR HFA inhaler

- When the counter reads 020, you should refill your prescription or ask your healthcare provider if you need another prescription for ADVAIR HFA.
- When the counter reads 000, throw the inhaler away. You should not keep using the inhaler when the counter reads 000 because you may not receive the right amount of medicine.
- Do not use the inhaler after the expiration date, which is on the packaging it comes in.

For correct use of your ADVAIR HFA inhaler, remember:

- The metal canister should always fit firmly in the plastic actuator.
- Breathe in deeply and slowly to make sure you get all the medicine.
- Hold your breath for about 10 seconds after breathing in the medicine. Then breathe out fully.
- After each dose, rinse your mouth with water and spit it out. Do not swallow the water.
- Do not take the inhaler apart.
- Always keep the protective cap on the mouthpiece when your inhaler is not in use.
- Always store your inhaler with the mouthpiece pointing down.
- Clean your inhaler at least 1 time each week.

For more information about ADVAIR HFA or how to use your inhaler, call 1-888-825-5249.

Trademarks are owned by or licensed to the GSK group of companies.

GlaxoSmithKline, Durham, NC 27701

©2023 GSK group of companies or its licensor.

ADH:7IFU

This Instructions for Use has been approved by the U.S. Food and Drug Administration Revised: July 2023

MEDICATION GUIDE

ADVAIR® [ad′ vair] HFA

(fluticasone propionate and salmeterol)

inhalation aerosol

for oral inhalation

What is the most important information I should know about ADVAIR HFA?

ADVAIR HFA can cause serious side effects, including:

- People with asthma who take long-acting beta2-adrenergic agonist (LABA) medicines, such as salmeterol (one of the medicines in ADVAIR HFA), have an increased risk of death from asthma problems. It is not known whether fluticasone propionate, the other medicine in ADVAIR HFA, reduces the risk of death from asthma problems seen with salmeterol.
- Call your healthcare provider if breathing problems worsen over time while using ADVAIR HFA. You may need different treatment.
- Get emergency medical care if:
  - your breathing problems worsen quickly.
  - you use your rescue inhaler, but it does not relieve your breathing problems.
- ADVAIR HFA should be used only if your healthcare provider decides that your asthma is not well controlled with a long-term asthma control medicine, such as an inhaled corticosteroid.
- When your asthma is well controlled, your healthcare provider may tell you to stop taking ADVAIR HFA. Your healthcare provider will decide if you can stop ADVAIR HFA without loss of asthma control. Your healthcare provider may prescribe a different asthma control medicine for you, such as an inhaled corticosteroid.
- Children and adolescents who take LABA medicines may have an increased risk of being hospitalized for asthma problems.

What is ADVAIR HFA?

- ADVAIR HFA combines the inhaled corticosteroid (ICS) medicine fluticasone propionate and the LABA medicine salmeterol.
- ICS medicines such as fluticasone propionate help to decrease inflammation in the lungs. Inflammation in the lungs can lead to breathing problems.
- LABA medicines such as salmeterol help the muscles around the airways in your lungs stay relaxed to prevent symptoms, such as wheezing, cough, chest tightness, and shortness of breath. These symptoms can happen when the muscles around the airways tighten. This makes it hard to breathe.
- ADVAIR HFA is not used to relieve sudden breathing problems.
- It is not known if ADVAIR HFA is safe and effective in children younger than 12 years of age.
- ADVAIR HFA is used for asthma as follows:
  - ADVAIR HFA is a prescription medicine used to control symptoms of asthma and to prevent symptoms such as wheezing in adults and adolescents aged 12 years and older.
  - ADVAIR HFA contains salmeterol, the same medicine found in SEREVENT® DISKUS® (salmeterol xinafoate inhalation powder). LABA medicines such as salmeterol increase the risk of death from asthma problems.
  - ADVAIR HFA is not for adults and adolescents with asthma who are well controlled with an asthma control medicine, such as a low to medium dose of an inhaled corticosteroid medicine.

Who should not use ADVAIR HFA?

Do not use ADVAIR HFA if you:

- are allergic to fluticasone propionate, salmeterol, or any of the ingredients in ADVAIR HFA. See “What are the ingredients in ADVAIR HFA?” below for a complete list of ingredients.

What should I tell my healthcare provider before using ADVAIR HFA?

Tell your healthcare provider about all of your health conditions, including if you:

- have heart problems.
- have high blood pressure.
- have seizures.
- have thyroid problems.
- have diabetes.
- have liver problems.
- have weak bones (osteoporosis).
- have an immune system problem.
- have eye problems such as glaucoma or cataracts.
- are allergic to any of the ingredients in ADVAIR HFA or any other medicines. See “What are the ingredients in ADVAIR HFA?” below for a complete list of ingredients.
- have any type of viral, bacterial, or fungal infection.
- are exposed to chickenpox or measles.
- have any other medical conditions.
- are pregnant or planning to become pregnant. It is not known if ADVAIR HFA may harm your unborn baby.
- are breastfeeding. It is not known if the medicines in ADVAIR HFA pass into your milk and if they can harm your baby.

Tell your healthcare provider about all the medicines you take, including prescription and over-the-counter medicines, vitamins, and herbal supplements. ADVAIR HFA and certain other medicines may interact with each other. This may cause serious side effects. Especially, tell your healthcare provider if you take antifungal or anti-HIV medicines.

Know the medicines you take. Keep a list of them to show your healthcare provider and pharmacist when you get a new medicine.

How should I use ADVAIR HFA?

Read the step-by-step instructions for using ADVAIR HFA at the end of this Medication Guide.

What should I avoid while using ADVAIR HFA?

- Do not use ADVAIR HFA unless your healthcare provider has taught you how to use the inhaler and you understand how to use it correctly.
- ADVAIR HFA comes in 3 different strengths. Your healthcare provider prescribed the strength that is best for you.
- Use ADVAIR HFA exactly as your healthcare provider tells you to use it. Do not use ADVAIR HFA more often than prescribed.
- Use 2 inhalations of ADVAIR HFA 2 times each day. Use ADVAIR HFA at the same time each day, about 12 hours apart.
- If you miss a dose of ADVAIR HFA, just skip that dose. Take your next dose at your usual time. Do not take 2 doses at 1 time.
- If you take too much ADVAIR HFA, call your healthcare provider or go to the nearest hospital emergency room right away if you have any unusual symptoms, such as worsening shortness of breath, chest pain, increased heart rate, or shakiness.
- Do not use other medicines that contain a LABA for any reason. Ask your healthcare provider or pharmacist if any of your other medicines are LABA medicines.
- Do not stop using ADVAIR HFA, even if you are feeling better, unless your healthcare provider tells you to.
- Talk to your healthcare provider right away if you stop using ADVAIR HFA.
- ADVAIR HFA does not relieve sudden breathing problems. Always have a rescue inhaler with you to treat sudden symptoms. If you do not have a rescue inhaler, call your healthcare provider to have one prescribed for you.
- Call your healthcare provider or get medical care right away if:
  - your breathing problems get worse.
  - you need to use your rescue inhaler more often than usual.
  - your rescue inhaler does not work as well to relieve your symptoms.
  - you need to use 4 or more inhalations of your rescue inhaler in 24 hours for 2 or more days in a row.
  - you use 1 whole canister of your rescue inhaler in 8 weeks.
  - your peak flow meter results decrease. Your healthcare provider will tell you the numbers that are right for you.
  - you have asthma and your symptoms do not improve after using ADVAIR HFA regularly for 1 week.

What are the possible side effects of ADVAIR HFA?

ADVAIR HFA can cause serious side effects, including:

- See “What is the most important information I should know about ADVAIR HFA?”
- fungal infection in your mouth or throat (thrush). Rinse your mouth with water without swallowing after using ADVAIR HFA to help decrease your chance of getting thrush.
- pneumonia. ADVAIR HFA contains the same medicine found in ADVAIR DISKUS® (fluticasone propionate and salmeterol inhalation powder). ADVAIR DISKUS is used to treat people with asthma and people with chronic obstructive pulmonary disease (COPD). People with COPD have a higher chance of getting pneumonia. ADVAIR DISKUS may increase the chance of you getting pneumonia. It is not known if ADVAIR HFA is safe and effective in people with COPD. Call your healthcare provider right away if you have any of the following symptoms:

• increase in mucus (sputum) production • chills

• change in mucus color • increased cough

• fever • increased breathing problems

- weakened immune system and increased chance of getting infections (immunosuppression).
- reduced adrenal function (adrenal insufficiency). Adrenal insufficiency is a condition where the adrenal glands do not make enough steroid hormones. This can happen when you stop taking oral corticosteroid medicines (such as prednisone) and start taking a medicine containing an inhaled steroid (such as ADVAIR HFA). During this transition period, when your body is under stress such as from fever, trauma (such as a car accident), infection, surgery, or worse COPD symptoms, adrenal insufficiency can get worse and may cause death.
  - Symptoms of adrenal insufficiency include:

• feeling tired • nausea and vomiting

• lack of energy • low blood pressure

• weakness

- sudden breathing problems immediately after inhaling your medicine. If you have sudden breathing problems immediately after inhaling your medicine, stop using ADVAIR HFA and call your healthcare provider right away.
- serious allergic reactions. Call your healthcare provider or get emergency medical care if you get any of the following symptoms of a serious allergic reaction:

• rash • swelling of your face, mouth and tongue

• hives • breathing problems

- effects on heart.

• increased blood pressure • chest pain

• a fast or irregular heartbeat

- effects on nervous system.

• tremor • nervousness

- bone thinning or weakness (osteoporosis).
- slowed growth in children. A child’s growth should be checked often.
- eye problems including glaucoma and cataracts. You should have regular eye exams while using ADVAIR HFA.
- changes in laboratory blood levels (sugar, potassium, certain types of white blood cells).

Common side effects of ADVAIR HFA include:

• upper respiratory tract infection • headache

• throat irritation • dizziness

• hoarseness and voice changes • nausea and vomiting

Tell your healthcare provider about any side effect that bothers you or that does not go away.

These are not all the side effects with ADVAIR HFA. Ask your healthcare provider or pharmacist for more information.

Call your doctor for medical advice about side effects. You may report side effects to FDA at 1-800-FDA-1088.

How should I store ADVAIR HFA?

- Store ADVAIR HFA at room temperature between 68°F and 77°F (20°C and 25°C) with the mouthpiece down.
- The contents of your ADVAIR HFA are under pressure: Do not puncture. Do not use or store near heat or open flame. Temperatures above 120°F may cause the canister to burst.
- Do not throw into fire or an incinerator.
- Safely throw away ADVAIR HFA in the trash when the counter reads 000.
- Keep ADVAIR HFA and all medicines out of the reach of children.

General information about the safe and effective use of ADVAIR HFA.

Medicines are sometimes prescribed for purposes not mentioned in a Medication Guide. Do not use ADVAIR HFA for a condition for which it was not prescribed. Do not give your ADVAIR HFA to other people, even if they have the same condition that you have. It may harm them.

This Medication Guide summarizes the most important information about ADVAIR HFA. If you would like more information, talk with your healthcare provider or pharmacist. You can ask your healthcare provider or pharmacist for information about ADVAIR HFA that was written for healthcare professionals.

What are the ingredients in ADVAIR HFA?

Active ingredients: fluticasone propionate, salmeterol xinafoate

Inactive ingredient: propellant HFA-134a

For more information about ADVAIR HFA, call 1-888-825-5249 or visit our website at www.advair.com.

ADVAIR, ADVAIR DISKUS, DISKUS, and SEREVENT are registered trademarks of the GSK group of companies.

GlaxoSmithKline

Research Triangle Park, NC 27709

©2017 the GSK group of companies. All rights reserved.

ADH:11MG

This Medication Guide has been approved by the U.S. Food and Drug Administration. Revised: February 2017